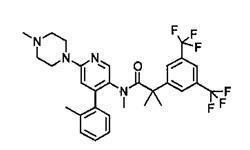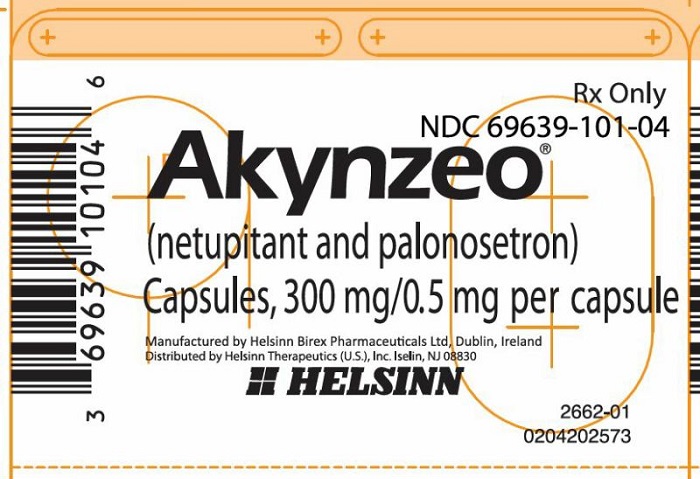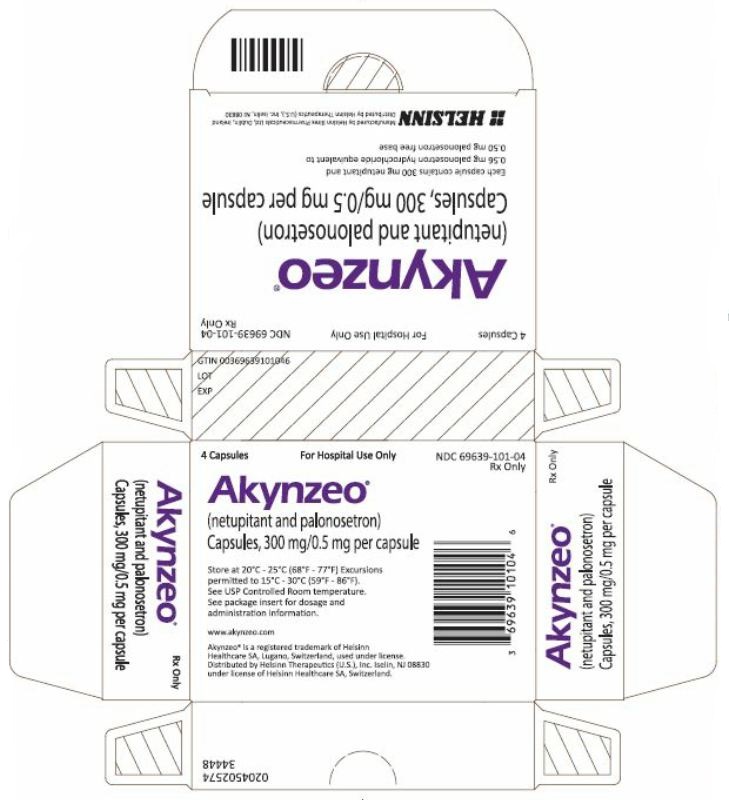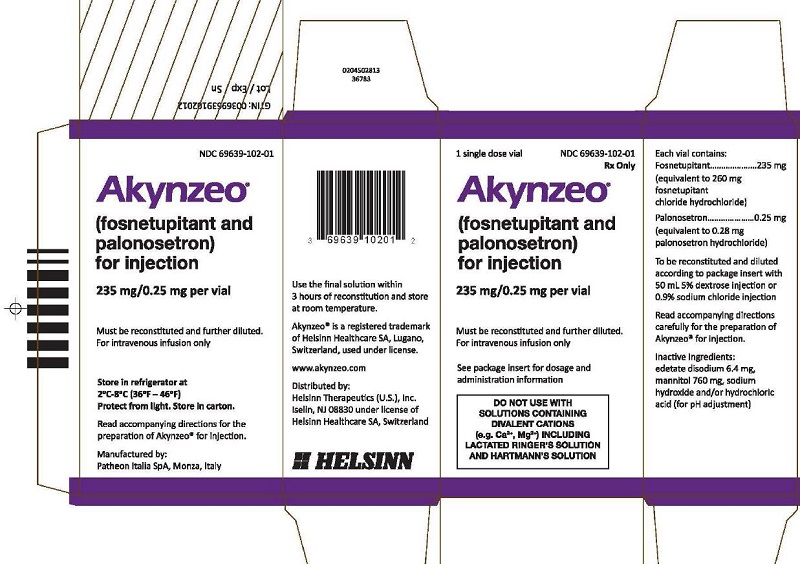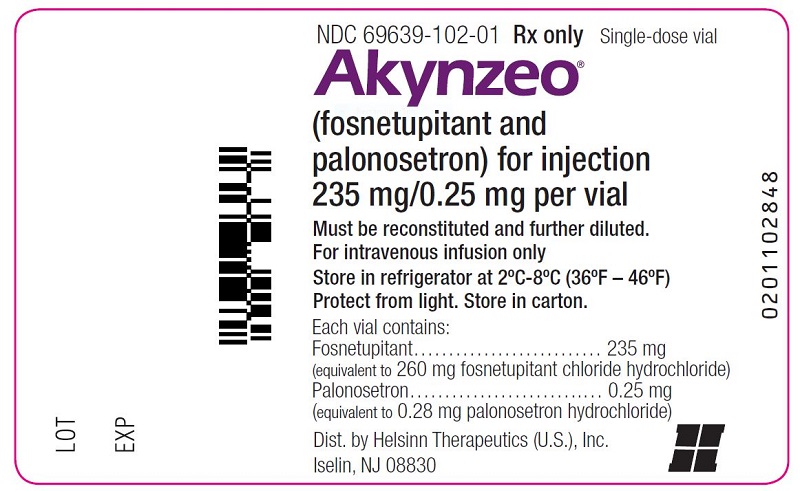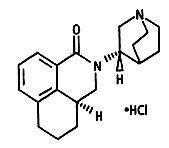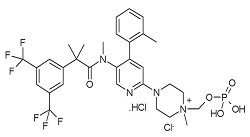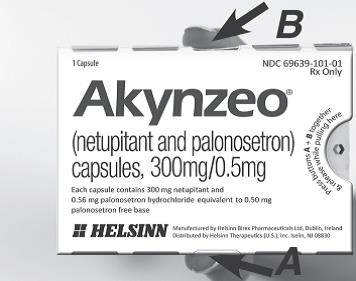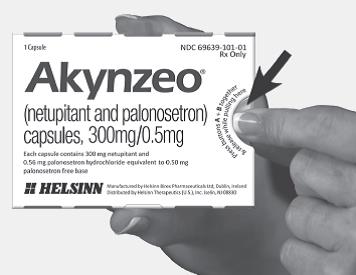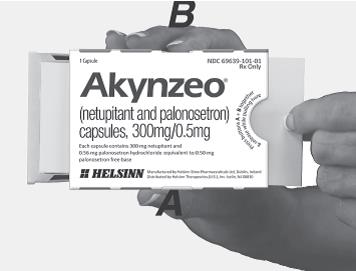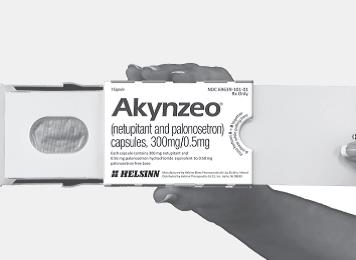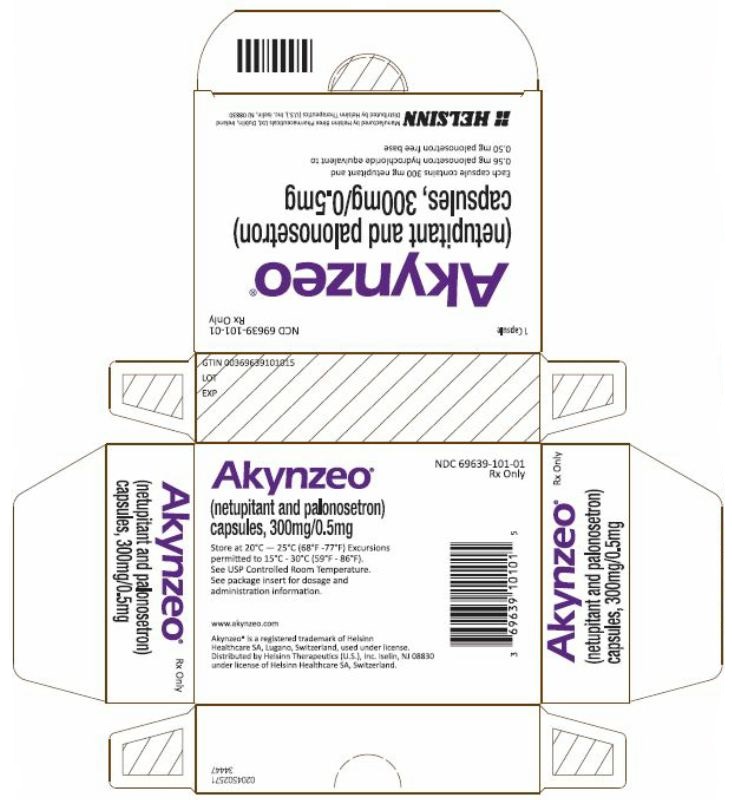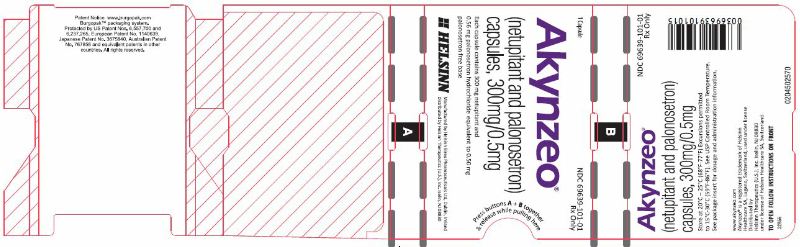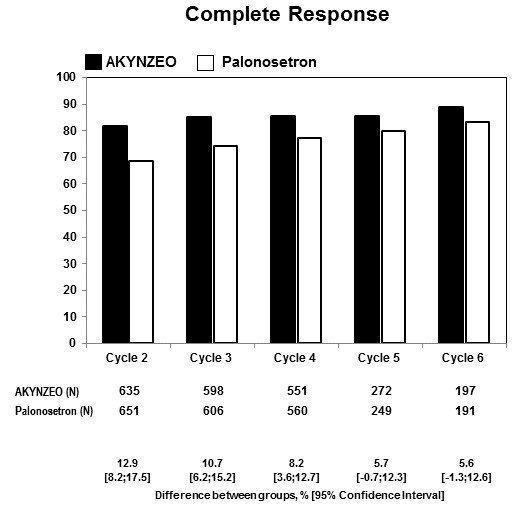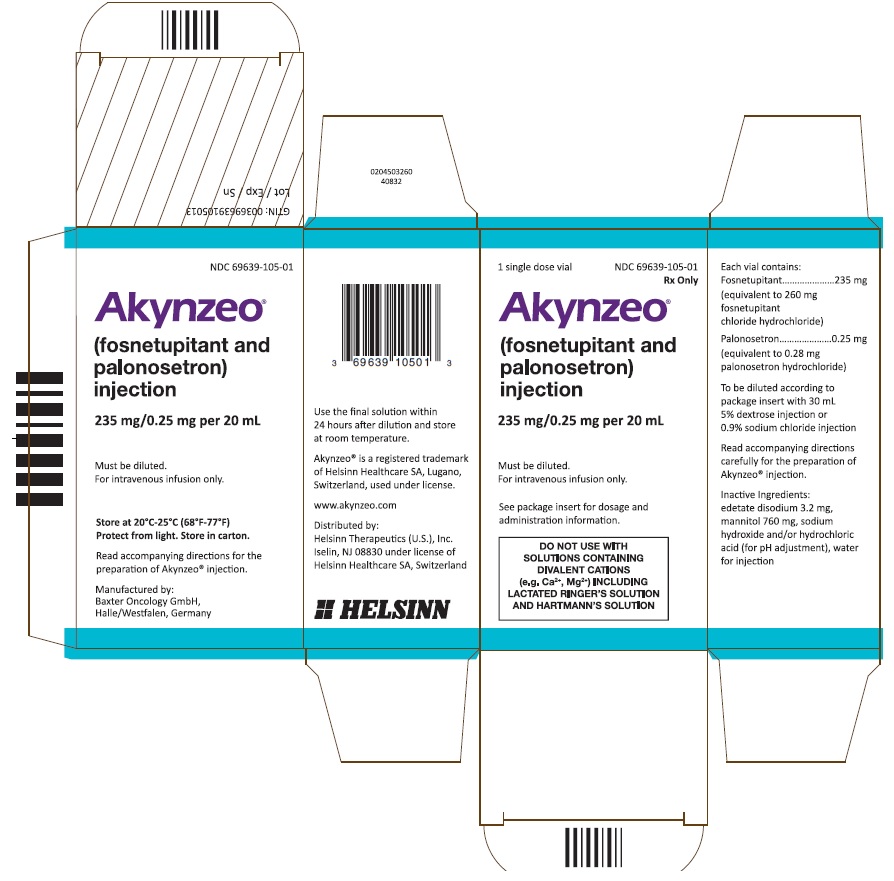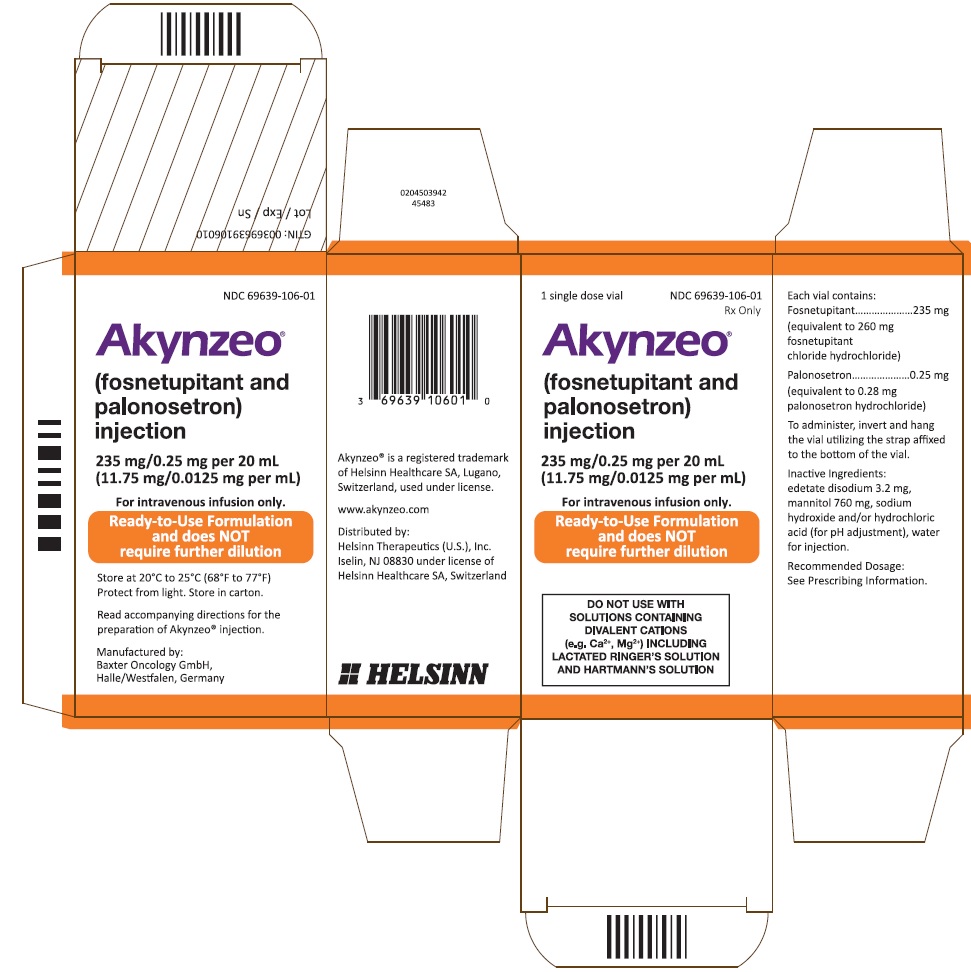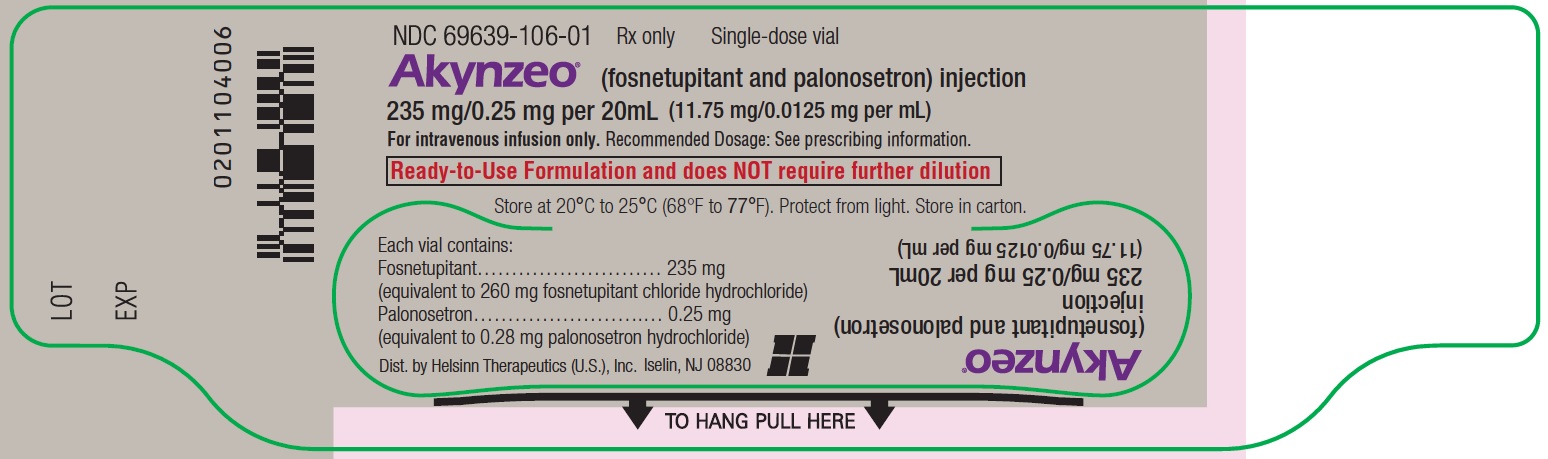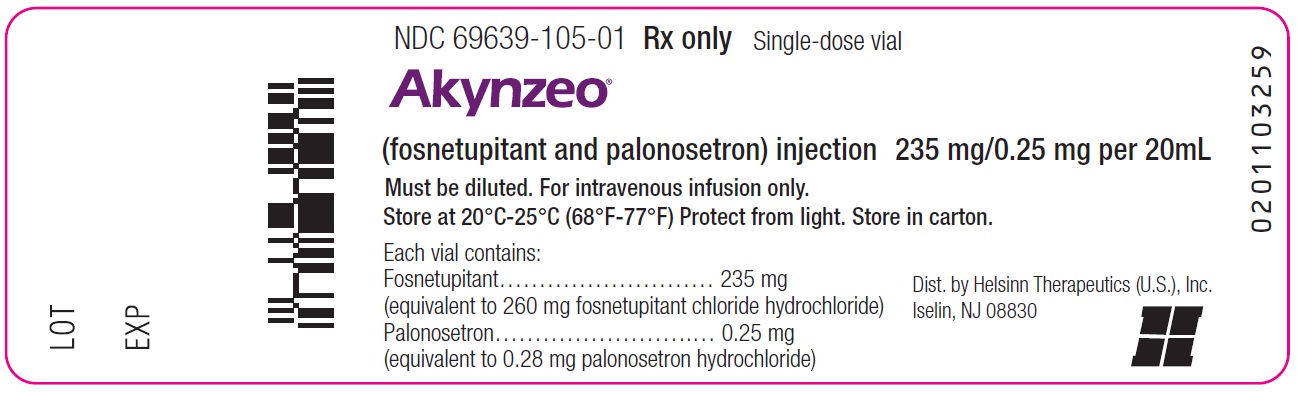 DRUG LABEL: AKYNZEO
NDC: 69639-101 | Form: CAPSULE
Manufacturer: Helsinn Therapeutics (U.S.), Inc.
Category: prescription | Type: HUMAN PRESCRIPTION DRUG LABEL
Date: 20260126

ACTIVE INGREDIENTS: NETUPITANT 300 mg/1 1; PALONOSETRON 0.5 mg/1 1
INACTIVE INGREDIENTS: CELLULOSE, MICROCRYSTALLINE; SUCROSE LAURATE; POVIDONE K30; CROSCARMELLOSE SODIUM; WATER; SILICON DIOXIDE; SODIUM STEARYL FUMARATE; MAGNESIUM STEARATE; CAPRYLIC/CAPRIC MONO/DIGLYCERIDES; GLYCERIN; POLYGLYCERYL-3 DIOLEATE; BUTYLATED HYDROXYANISOLE; GELATIN; SORBITOL; TITANIUM DIOXIDE; FERRIC OXIDE YELLOW; FERRIC OXIDE RED

HIGHLIGHTS OF PRESCRIBING INFORMATION

These highlights do not include all the information needed to use AKYNZEO® safely and effectively. See full prescribing information for AKYNZEO®.
AKYNZEO® (netupitant and palonosetron) capsules, for oral use
Initial U.S. Approval: 2014
AKYNZEO® (fosnetupitant and palonosetron) for injection, for intravenous use
Initial U.S. Approval: 2018

1 INDICATIONS AND USAGE

- AKYNZEO capsules is indicated in combination with dexamethasone in adults for the prevention of acute and delayed nausea and vomiting associated with initial and repeat courses of cancer chemotherapy, including, but not limited to, highly emetogenic chemotherapy.
- AKYNZEO for injection and AKYNZEO injection are indicated in combination with dexamethasone in adults for the prevention of acute and
  delayed nausea and vomiting associated with initial and repeat courses of highly emetogenic cancer chemotherapy.
  Limitations of Use
  - AKYNZEO for injection and AKYNZEO injection have not been studied for the prevention of nausea and vomiting associated with anthracycline plus cyclophosphamide chemotherapy.
- AKYNZEO is a combination of palonosetron, a serotonin-3 (5-HT3) receptor antagonist, and netupitant or fosnetupitant, substance P/neurokinin-1 (NK-1) receptor antagonists: palonosetron prevents nausea and vomiting during the acute phase and netupitant/fosnetupitant prevents nausea and vomiting during both the acute and delayed phase after cancer chemotherapy. (1)

2 DOSAGE AND ADMINISTRATION

Recommended Dosage

- AKYNZEO capsules: The recommended dosage is one AKYNZEO capsule administered 1 hour prior to the start of chemotherapy, with or without food. (2.1)

Preparation and Administration

- AKYNZEO injection is supplied either as a Ready-to-Use (with hanger) vial or a To-be-Diluted vial. (2.2)
- AKYNZEO for injection requires dilution prior to administration. (2.3)
- See full prescribing information for information on preparation, administration, and incompatibilities for each product. (2.2, 2.3, 2.4)

3 DOSAGE FORMS AND STRENGTHS

- Capsules: 300 mg netupitant/0.5 mg palonosetron. (3)
- For Injection: 235 mg fosnetupitant/0.25 mg palonosetron as a lyophilized powder in single-dose vial for reconstitution. (3)
- Injection: 235 mg fosnetupitant/0.25 mg palonosetron (235 mg/0.25 mg per 20 mL (11.75 mg/0.0125 mg per mL) solution in single-dose vial. (3)
  - Ready-to-Use (with hanger)
  - To-be-Diluted

4 CONTRAINDICATIONS

None (4)

5 WARNINGS AND PRECAUTIONS

- Hypersensitivity reactions, including anaphylaxis, have been reported in patients receiving palonosetron, one of the components of AKYNZEO, with or without known hypersensitivity to other 5-HT3 receptor antagonists. (5.1)
- Serotonin syndrome has been reported with 5-HT3 receptor antagonists alone but particularly with concomitant use of serotonergic drugs. If such symptoms occur, discontinue AKYNZEO and initiate supportive treatment. If concomitant use of AKYNZEO with other serotonergic drugs is clinically warranted, patients should be made aware of a potential increased risk for serotonin syndrome. (5.2,7.3)

6 ADVERSE REACTIONS

Most common adverse reactions (≥3%) for AKYNZEO capsules are headache, asthenia, dyspepsia, fatigue, constipation and erythema (6.1)

The safety profile of AKYNZEO for injection was generally similar to that seen with AKYNZEO capsules. (6.1)

To report SUSPECTED ADVERSE REACTIONS, contact HELSINN at 1-844-357-4668 or FDA at 1-800-FDA-1088 or www.fda.gov/medwatch.

7 DRUG INTERACTIONS

- CYP3A4 Substrates: inhibition of CYP3A4 by netupitant can result in increased plasma concentrations of the concomitant drug for 6 days after single dosage administration of AKYNZEO; avoid concomitant CYP3A4 substrates for one week, if feasible. If not avoidable, consider dose reduction of the CYP3A4 substrate (7.1)
- CYP3A4 Inducers (e.g., rifampin): decreased plasma concentrations of netupitant; avoid use (7.2)

8 USE IN SPECIFIC POPULATIONS

- Pregnancy: May cause fetal harm (8.1).
- Hepatic Impairment: Avoid use in patients with severe hepatic impairment (8.6)
- Renal Impairment: Avoid use in patients with severe renal impairment or end-stage renal disease (8.7)

FULL PRESCRIBING INFORMATION

1 INDICATIONS AND USAGE

- AKYNZEO capsules is indicated in combination with dexamethasone in adults for the prevention of acute and delayed nausea and vomiting associated with initial and repeat courses of cancer chemotherapy, including, but not limited to, highly emetogenic chemotherapy. AKYNZEO capsules is a combination of palonosetron and netupitant: palonosetron prevents nausea and vomiting during the acute phase and netupitant prevents nausea and vomiting during both the acute and delayed phase after cancer chemotherapy.
- AKYNZEO for injection and AKYNZEO injection are indicated in combination with dexamethasone in adults for the prevention of acute and delayed nausea and vomiting associated with initial and repeat courses of highly emetogenic cancer chemotherapy. AKYNZEO for injection is a combination of palonosetron and fosnetupitant, a prodrug of netupitant: palonosetron prevents nausea and vomiting during the acute phase and fosnetupitant prevents nausea and vomiting during both the acute and delayed phase after cancer chemotherapy.
  Limitations of Use
  AKYNZEO for injection and AKYNZEO injection have not been studied for the prevention of nausea and vomiting associated with anthracycline plus cyclophosphamide chemotherapy.

2 DOSAGE AND ADMINISTRATION

2.1 Recommended Dosage

The recommended dosages of AKYNZEO and dexamethasone in adults for the prevention of nausea and vomiting associated with administration of emetogenic chemotherapy are shown in Table 1.

AKYNZEO capsules can be taken with or without food.

Table 1: Antiemetic Treatment Regimen
Treatment Regimen | Day 1 |  | Days 2 to 4
Highly Emetogenic Chemotherapy, including Cisplatin-Based Chemotherapy
AKYNZEO capsules | 1 capsule of AKYNZEO | 1 hour before chemotherapy | Dexamethasone 8 mg once a day
AKYNZEO capsules | Dexamethasone 12 mg | 30 minutes before chemotherapy | Dexamethasone 8 mg once a day
AKYNZEO for injection and AKYNZEO injection | 1 vial of AKYNZEO | Infuse over 30 minutes starting 30 minutes before chemotherapy [see Dosage and Administration (2.2)] | Dexamethasone 8 mg once a day
AKYNZEO for injection and AKYNZEO injection | Dexamethasone 12 mg | 30 minutes before chemotherapy | Dexamethasone 8 mg once a day
Anthracyclines and Cyclophosphamide-Based Chemotherapy and Chemotherapy Not Considered Highly Emetogenic
AKYNZEO capsules | 1 capsule of AKYNZEO | 1 hour before chemotherapy | None
AKYNZEO capsules | Dexamethasone 12 mg | 30 minutes before chemotherapy | None

2.2 Preparation and Administration of AKYNZEO Injection (Ready-to-Use and To-be-Diluted)

AKYNZEO injection is supplied as either a Ready-to-Use (with hanger) vial or a To-be-Diluted vial.

AKYNZEO injection (Ready-to-Use; with hanger)
See Table 2 for preparation instructions of AKYNZEO injection (Ready-to-Use) for intravenous infusion. AKYNZEO injection (Ready-to-Use) does not require dilution prior to administration.

Table 2: Preparation and Administration of AKYNZEO Injection (Ready-to-Use) for Intravenous Infusion
Step 1 | Before administration, inspect the solution for particulate matter and discoloration. Discard the vial if particulates and/or discoloration are observed.
Step 2 | Using aseptic technique, insert a vented intravenous set through the septum of the vial. Once the stopper is punctured, use immediately.
Step 3 | To administer, invert and hang the vial utilizing the strap affixed to the bottom of the vial.
Step 4 | Administer over 30 minutes as an intravenous infusion. At the end of the infusion, flush the infusion line with 0.9% Sodium Chloride Injection, USP or with 5% Dextrose injection, USP to ensure complete drug administration.

AKYNZEO injection (Ready-to-Use) contains no antimicrobial preservatives and is intended for single use only.

Compatibility
AKYNZEO injection (Ready-to-Use) is compatible with intravenous dexamethasone sodium phosphate which can be infused simultaneously. Do not add dexamethasone sodium phosphate to the AKYNZEO injection (Ready-to-Use) vial.

Stability and Storage
Use immediately once the stopper is punctured.

AKYNZEO Injection (To-be-Diluted)
See Table 3 for preparation instructions of AKYNZEO injection (To-be-Diluted) for intravenous infusion with dilution.

Table 3: Preparation and Administration of AKYNZEO Injection (To-be-Diluted) for Intravenous Infusion
Step 1 | Before administration, inspect the solution for particulate matter and discoloration. Discard the vial if particulates and/or discoloration are observed.
Step 2 | Aseptically prepare an infusion vial or bag filled with 30 mL of 5% Dextrose injection, USP or 0.9% Sodium Chloride injection, USP.
Step 3 | Aseptically withdraw the entire volume of solution from the AKYNZEO vial (20 mL) and transfer it into the infusion vial or bag containing 30 mL of 5% Dextrose injection, USP or 0.9% Sodium Chloride injection, USP to yield a total volume of 50 mL.
Step 4 | Gently invert the vial or bag until complete dissolution.
Step 5 | Before administration, inspect the final diluted solution for particulate matter and discoloration. Discard the vial or bag if particulates and/or discoloration are observed.
Step 6 | Administer over 30 minutes as an intravenous infusion. At the end of the infusion, flush the infusion line with the same carrier solution to ensure complete drug administration.

AKYNZEO injection (To-be-Diluted) contains no antimicrobial preservatives and is intended for single use only.

Compatibility

AKYNZEO injection (To-be-Diluted) is compatible with intravenous dexamethasone sodium phosphate which can be added to the infusion bag containing AKYNZEO solution or infused simultaneously.

Stability and Storage

The total time from dilution to the start of the infusion, with or without intravenous dexamethasone sodium phosphate, should not exceed 24 hours.

Store the final diluted solution at room temperature, 20ºC to 25ºC (68Fº to 77ºF).

2.3 Preparation and Administration of AKYNZEO for Injection

See Table 4 for preparation instructions of AKYZNEO for injection. AKYNZEO for injection requires dilution prior to administration.

Table 4: Preparation and Administration of AKYNZEO for Injection
Step 1 | Aseptically inject 20 mL 5% Dextrose injection, USP or 0.9% Sodium Chloride injection, USP into the vial. Ensure the solvent is added to the vial along the vial wall and not jetted in order to prevent foaming. Swirl the vial gently.
Step 2 | Aseptically prepare an infusion vial or bag filled with 30 mL of 5% Dextrose injection, USP or 0.9% Sodium Chloride injection, USP.
Step 3 | Aseptically withdraw the entire volume of solution from the AKYNZEO vial and transfer it into the infusion vial or bag containing 30 mL of 5% Dextrose injection, USP or 0.9% Sodium Chloride injection, USP to yield a total volume of 50 mL.
Step 4 | Gently invert the vial or bag until complete dissolution.
Step 5 | Before administration, inspect the final diluted solution for particulate matter and discoloration. Discard the vial or bag if particulates and/or discoloration are observed.
Step 6 | Administer over 30 minutes as an intravenous infusion. At the end of the infusion, flush the infusion line with the same carrier solution to ensure complete drug administration.

AKYNZEO for injection contains no antimicrobial preservatives, is intended for single use only.

Compatibility

AKYNZEO for injection is compatible with intravenous dexamethasone sodium phosphate which can be added to the infusion bag containing AKYNZEO solution or infused simultaneously.

Stability and Storage

The total time from reconstitution to the start of the infusion, with or without intravenous dexamethasone sodium phosphate, should not exceed 24 hours.

Store the reconstituted solution and the final diluted solution at room temperature, 20ºC to 25ºC (68ºF to 77ºF).

2.4 Incompatibility of AKYNZEO for Injection and AKYZNEO Injection

AKYNZEO for injection, AKYNZEO injection (Ready-to-Use) and AKYNZEO injection (To-be-Diluted) are incompatible with any solution containing divalent cations (e.g., calcium, magnesium), including Lactated Ringer’s injection and Hartmann's Solution.

Limited data are available on the compatibility of AKYNZEO for injection, AKYNZEO injection (Ready-to-Use), and AKYNZEO injection (To-be-Diluted) with other intravenous substances, additives, or other medications with the exception of intravenous dexamethasone sodium phosphate [see Dosage and Administration (2.2, 2.3)] and they should not be added to the AKYNZEO solution or infused simultaneously. If the same intravenous line is used for sequential infusion of several different drugs, flush the line before and after infusion of AKYNZEO solution with 0.9% Sodium Chloride Injection, USP.

3 DOSAGE FORMS AND STRENGTHS

- Capsules: 300 mg netupitant/0.5 mg palonosetron in a hard gelatin capsule with white body and caramel cap with “HE1” printed on the body.
- For Injection: 235 mg fosnetupitant/0.25 mg palonosetron white to off-white lyophilized powder in single-dose vial for reconstitution.
- Injection: 235 mg fosnetupitant/0.25 mg palonosetron per 20 mL (11.75 mg/0.0125 mg per mL) as a clear solution in single-dose vial.
  - Ready-to-Use (with hanger)
  - To-be-Diluted

4 CONTRAINDICATIONS

None.

5 WARNINGS AND PRECAUTIONS

5.1 Hypersensitivity

Hypersensitivity reactions, including anaphylaxis, have been reported in patients treated with palonosetron, one of the components of AKYNZEO, with or without known hypersensitivity to other 5-HT3 receptor antagonists.

5.2 Serotonin Syndrome

The development of serotonin syndrome has been reported with 5-HT3 receptor antagonists. Most reports have been associated with concomitant use of serotonergic drugs (e.g., selective serotonin reuptake inhibitors (SSRIs), serotonin and norepinephrine reuptake inhibitors (SNRIs), monoamine oxidase inhibitors, mirtazapine, fentanyl, lithium, tramadol, and intravenous methylene blue). Some of the reported cases were fatal. Serotonin syndrome occurring with overdose of another 5-HT3 receptor antagonist alone has also been reported. The majority of reports of serotonin syndrome related to 5-HT3 receptor antagonist use occurred in a post-anesthesia care unit or an infusion center.

Symptoms associated with serotonin syndrome may include the following combination of signs and symptoms: mental status changes (e.g., agitation, hallucinations, delirium, and coma), autonomic instability (e.g., tachycardia, labile blood pressure, dizziness, diaphoresis, flushing, and hyperthermia), neuromuscular symptoms (e.g., tremor, rigidity, myoclonus, hyperreflexia, and incoordination), seizures, with or without gastrointestinal symptoms (e.g., nausea, vomiting, diarrhea). Patients should be monitored for the emergence of serotonin syndrome, especially with concomitant use of AKYNZEO and other serotonergic drugs. If symptoms of serotonin syndrome occur, discontinue AKYNZEO and initiate supportive treatment. Patients should be informed of the increased risk of serotonin syndrome, especially if AKYNZEO is used concomitantly with other serotonergic drugs [see Drug Interactions (7.3)].

6 ADVERSE REACTIONS

The following clinically significant adverse reactions are found elsewhere in the labeling:

- Hypersensitivity Reactions [see Warnings and Precautions (5.1)]
- Serotonin Syndrome [see Warnings and Precautions (5.2)]

6.1 Clinical Trials Experience

Because clinical trials are conducted under widely varying conditions, adverse reaction rates observed in the clinical trials of a drug cannot be directly compared to rates in the clinical trials of another drug and may not reflect the rates observed in practice.

AKYNZEO Capsules

The overall safety of AKYNZEO capsules was evaluated in 1538 cancer patients and healthy subjects in clinical trials. The data described below reflect exposure to AKYNZEO in 1169 cancer patients, receiving at least one cycle of cancer chemotherapy in 3 active-controlled trials [see Clinical Studies (14.1)], including 782 exposed to AKYNZEO for at least 4 cycles and 321 exposed for at least 6 cycles, up to a maximum of 12 cycles of chemotherapy. The median age was 55, 79% were female, 83% were White, 13% were Asian, and 4% were Hispanic. All patients received a single oral dose of AKYNZEO 1 hour prior to the start of each chemotherapy cycle. In all studies, dexamethasone was co-administered with AKYNZEO [see Clinical Studies (14.1), Table 16 and Table 18].

Cisplatin Based Highly Emetogenic Chemotherapy

In a single-cycle study of patients receiving cisplatin based highly emetogenic chemotherapy, 136 patients were treated with AKYNZEO. Table 5 shows adverse reactions reported at an incidence of at least 3% and for which the AKYNZEO rate exceeded palonosetron alone.

Table 5: Adverse Reactions Occurring in ≥3% of Cancer Patients Receiving AKYNZEO capsules and Cisplatin Based Highly Emetogenic Chemotherapy (Cycle 1)
Adverse Reactions | AKYNZEO netupitant 300 mg/palonosetron 0.5 mg (N=136) | Palonosetron 0.5 mg (N=136)
Dyspepsia | 4% | 2%
Fatigue | 4% | 2%
Constipation | 3% | 1%
Erythema | 3% | 2%

Anthracyclines and Cyclophosphamide Based Chemotherapy

In a study of patients receiving anthracycline and cyclophosphamide based chemotherapy, 725 patients were treated with AKYNZEO capsules during Cycle 1, and 635 of these patients continued for up to 8 cycles in a multiple-cycle extension. Table 6 shows adverse reactions reported at an incidence of at least 3% and for which the AKYNZEO capsules rate exceeded palonosetron alone during Cycle 1. The adverse reaction profile in subsequent cycles was similar to that observed in Cycle 1.

Table 6: Adverse Reactions Occurring in ≥3% of Cancer Patients Receiving AKYNZEO capsules and Anthracyclines and Cyclophosphamide Based Chemotherapy (Cycle 1)
Adverse Reactions | AKYNZEO netupitant 300 mg/palonosetron 0.5 mg (N=725) | Palonosetron 0.5 mg (N=725)
Headache | 9% | 7%
Asthenia | 8% | 7%
Fatigue | 7% | 5%

In addition to the adverse reactions shown above, there were reports of concomitant elevations of transaminases greater than 3 times the upper limit of normal and total bilirubin in both arms of the two trials that compared AKYNZEO capsules to oral palonosetron, and the frequency of these elevations was comparable between treatment groups. See Table 7.

Table 7: Liver Function Laboratory Abnormalities
Laboratory Changes | AKYNZEO netupitant 300 mg/palonosetron 0.5 mg N=861 | Palonosetron 0.5 mg N=861
AST > 3 x ULN and/or ALT > 3 x ULN with Total Bilirubin > ULN | 3 (0.3%) | 5 (0.6%)
AST > 10 x ULN and/or ALT > 10 x ULN with Total Bilirubin > ULN | - | 2 (0.2%)
AST > 3 x ULN and/or ALT > 3 x ULN with Total Bilirubin ≥ 2 x ULN | 1 (0.1%) | 1 (0.1%)
ULN = upper limit of normal

In a multi-cycle safety study of 412 patients, the safety profile of AKYNZEO capsules (n = 308) was comparable to aprepitant and palonosetron (n = 104) in patients undergoing initial and repeat cycles (median 5 cycles, range of 1-14 cycles) of chemotherapy, including carboplatin, cisplatin, oxaliplatin, and doxorubicin regimens. There were no reports of concomitant elevations of transaminases greater than 3 times the upper limit of normal and total bilirubin in this study in either arm.

In a randomized, clinical non-inferiority study, that compared oral palonosetron 0.5 mg to intravenous palonosetron 0.25 mg in cancer patients scheduled to receive highly emetogenic cisplatin (greater than or equal to 70 mg/m^2) based chemotherapy, there were two patients (0.5%; 2/369) in the intravenous palonosetron arm who had concomitant elevations of transaminases and total bilirubin. Neither experienced transaminase elevations greater than 10 times the upper limit of normal.

AKYNZEO for Injection

The safety of AKYNZEO for injection was evaluated in 203 patients in an active-controlled multi-cycle (median 4 cycles, range of 1-4 cycles) safety clinical study in patients receiving HEC regimens, not including anthracycline plus cyclophosphamide, (e.g., cisplatin, cyclophosphamide, carmustine, dacarbazine and mechlorethamine) compared to 201 patients receiving AKYNZEO capsules (NCT02517021). The median age was 60 years, 46% were female, 99.5 % were White, 0.3% were Asian, and 0.3% were Hispanic. All patients received a single dose of AKYNZEO for injection 30 minutes prior to the start of each chemotherapy cycle; dexamethasone was co-administered with AKYNZEO. The safety profile of AKYNZEO for injection was generally similar to that seen with AKYNZEO capsules.

7 DRUG INTERACTIONS

7.1 Effects of AKYNZEO on Other Drugs

Interaction with CYP3A4 Substrates

Netupitant is a moderate inhibitor of CYP3A4.

AKYNZEO should be used with caution in patients receiving concomitant medications that are primarily metabolized through CYP3A4. A single oral dose of netupitant 300 mg significantly inhibits CYP3A4 for 6 days. Avoid concomitant use of drugs that are CYP3A4 substrates for one week, if feasible. If not avoidable, consider dose reduction of CYP3A4 substrates.

Dexamethasone

A single oral dose of netupitant 300 mg or a single fosnetupitant infusion of 235 mg increased the systemic exposure of concomitant dexamethasone more than 2-fold on Days 2 and 4. Administer a reduced dose of dexamethasone with AKYNZEO [see Dosage and Administration (2.1), Clinical Pharmacology (12.3)].

Midazolam

When administered with netupitant, the systemic exposure to midazolam was significantly increased. Consider the potential effects of increased plasma concentrations of midazolam or other benzodiazepines metabolized via CYP3A4 (alprazolam, triazolam) when administering these drugs with AKYNZEO [see Clinical Pharmacology (12.3)].

Chemotherapeutic Agents

The systemic exposure of chemotherapy agents metabolized by CYP3A4 can increase when administered with AKYNZEO. Chemotherapy agents that are known to be metabolized by CYP3A4 include docetaxel, paclitaxel, etoposide, irinotecan, cyclophosphamide, ifosfamide, imatinib, vinorelbine, vinblastine, and vincristine [see Clinical Pharmacology (12.3)]. Caution and monitoring for chemotherapeutic related adverse reactions are advised in patients receiving chemotherapy agents metabolized primarily by CYP3A4.

Oral Contraceptives

There is no clinically significant effect of AKYNZEO on the efficacy of oral contraceptives containing levonorgestrel and ethinyl estradiol [see Clinical Pharmacology (12.3)].

Warfarin

Although it was predicted that co-administration of intravenous AKYNZEO with warfarin would not substantially increase the systemic exposure to S-warfarin (CYP2C9 substrate), the active enantiomer, the effects of AKYNZEO for injection and AKYNZEO capsules on INR and prothrombin time have not been studied. Monitor INR and adjust the dosage of warfarin, as needed with concomitant use of AKYNZEO, to maintain the target INR range.

7.2 Effects of Other Drugs on AKYNZEO

Netupitant is mainly metabolized by CYP3A4.

Palonosetron is mainly metabolized by CYP2D6 and to a lesser extent by CYP3A4 and CYP1A2.

CYP3A4 Inducers

Avoid concomitant use of AKYNZEO in patients who are chronically using a strong CYP3A4 inducer such as rifampin. A strong CYP3A inducer can decrease the efficacy of AKYNZEO by substantially reducing plasma concentrations of the netupitant component [see Clinical Pharmacology (12.3)].

CYP3A4 Inhibitors

Concomitant use of AKYNZEO with a strong CYP3A4 inhibitor (e.g., ketoconazole) can increase the systemic exposure to the netupitant component of AKYNZEO. However, no dosage adjustment is necessary for single dose administration of AKYNZEO [see Clinical Pharmacology (12.3)].

7.3 Serotonergic Drugs

Serotonin syndrome (including altered mental status, autonomic instability, and neuromuscular symptoms) has been described following the concomitant use of 5-HT3 receptor antagonists and other serotonergic drugs, including selective serotonin reuptake inhibitors (SSRIs) and serotonin and noradrenaline reuptake inhibitors (SNRIs). If symptoms occur, discontinue AKYNZEO and initiate supportive treatment [see Warnings and Precautions (5.2)].

8 USE IN SPECIFIC POPULATIONS

8.1 Pregnancy

Risk Summary

Limited available data with AKYNZEO use in pregnant women are insufficient to inform a drug- associated risk of adverse developmental outcomes. In animal reproduction studies with netupitant, no effects on embryo-fetal development were observed following daily oral administration in pregnant rats during the period of organogenesis at doses up to 3.7 times the human AUC (area under the plasma concentration-time curve) at the recommended single dose to be given with each cycle of chemotherapy. However, a dose-dependent increase in adverse effects on embryo-fetal development was observed following daily oral administration of netupitant in pregnant rabbits during the period of organogenesis with doses at least 0.2 times the human AUC at the recommended single dose to be given with each cycle of chemotherapy. Daily oral administration of netupitant in rats up to 3.7 times the human AUC at the recommended dose during organogenesis through lactation produced no adverse effects in the offspring (see Data).

In animal reproduction studies with fosnetupitant, delayed ossification of pubis occurred after intravenous administration in rats during the period of organogenesis at a dose 3 times the human AUC for netupitant at the recommended single dose to be given with each cycle of chemotherapy. In pregnant rabbits, an increase in resorptions was observed with daily intravenous administration of fosnetupitant during the period of organogenesis at doses up to 9 times the human AUC for fosnetupitant and 0.4 times the human AUC for netupitant at the recommended single dose to be given with each cycle of chemotherapy. Daily intravenous administration of fosnetupitant (3 times the human AUC for netupitant at the recommended single dose to be given with each cycle of chemotherapy) in rats during organogenesis through lactation produced lower bodyweight in offspring at birth through maturation, and delayed physical development (see Data).

In animal reproduction studies with palonosetron, no effects on embryo-fetal development were observed following oral administration during the period of organogenesis at doses up to 921 and 1841 times the recommended oral dose in rats and rabbits, respectively (see Data).
Based on animal data from netupitant studies, advise pregnant women of the potential risk to a fetus.

The estimated background risk of major birth defects and miscarriage for the indicated populations are unknown. All pregnancies have a background risk of birth defect, loss, or other adverse outcomes. In the U.S. general population, the estimated background risk of major birth defects and miscarriage in clinically recognized pregnancies is 2 to 4% and 15 to 20%, respectively.

Data

Animal Data

Netupitant

Daily oral administration of up to 30 mg/kg netupitant in rats (3.7 times the human AUC at the recommended single dose to be given with each cycle of chemotherapy) during the period of organogenesis produced no effects on embryo-fetal development. However, an increased incidence of external and skeletal abnormalities in rabbit fetuses was observed following daily oral administration of netupitant in rabbits at 10 mg/kg/day and higher (0.2 times the human AUC at the recommended single dose to be given with each cycle of chemotherapy) during the period of organogenesis. These abnormalities included positional abnormalities in the limbs and paws, and fused sternebrae. Reduction in fetal rabbit weight occurred at 30 mg/kg/day. Maternal toxicity in rabbits (i.e., loss of bodyweight during the treatment period) was also observed at 30 mg/kg/day. Daily oral administration of up to 30 mg/kg netupitant (3.7 times the human AUC at the recommended dose) in rats during organogenesis through lactation produced no adverse effects in the offspring.

Fosnetupitant

Daily intravenous administration of 39 mg/kg/day fosnetupitant in rats (3 times the human AUC for netupitant at the recommended single dose to be given with each cycle of chemotherapy) during the period of organogenesis produced delayed ossification of pubis. No effects on embryo-fetal development were observed with daily administration of up to 13 mg/kg fosnetupitant in rats (2 times the human AUC for netupitant at the recommended single dose to be given with each cycle of chemotherapy). Due to the limited systemic exposure to fosnetupitant in pregnant rats, it is not possible to provide an AUC-based comparison of fosnetupitant exposure in rats and humans. An increase in resorptions was observed with daily intravenous administration of fosnetupitant at 6 mg/kg/day and higher in rabbits (9 times the human AUC for fosnetupitant and 0.4 times the human AUC for netupitant at the recommended single dose to be given with each cycle of chemotherapy) during the period of organogenesis. No effects were observed in rabbits at 3 mg/kg/day (5.4 times the human AUC for fosnetupitant and 0.4 times the human AUC for netupitant at the recommended single dose to be given with each cycle of chemotherapy). Daily intravenous administration of 39 mg/kg fosnetupitant in rats (3 times the AUC for netupitant at the recommended single dose to be given with each cycle of chemotherapy) during organogenesis through lactation produced lower bodyweight in offspring at birth through maturation, and delayed physical development (pinna detachment, eye opening, and preputial separation). These effects were associated with maternal toxicity (reduced weight gain and food consumption). No effects occurred in offspring or dams at 13 mg/kg/day (2 times the human AUC for netupitant at the recommended single dose to be given with each cycle of chemotherapy).

Palonosetron

In animal reproduction studies with palonosetron, no effects on embryo-fetal development were observed in pregnant rats given oral doses up to 60 mg/kg/day (921 times the recommended oral dose based on body surface area) or pregnant rabbits given oral doses up to 60 mg/kg/day (1841 times the recommended oral dose based on body surface area) during the period of organogenesis.

8.2 Lactation

Risk Summary

There are no data on the presence of netupitant (or fosnetupitant) or palonosetron in human milk, the effects on the breastfed infant, or the effects on milk production. The developmental and health benefits of breastfeeding should be considered along with the mother’s clinical need for AKYNZEO and any potential adverse effect on the breastfed child from AKYNZEO or from the underlying maternal condition.

8.4 Pediatric Use

The safety and effectiveness of AKYNZEO in patients below the age of 18 years have not been established.

8.5 Geriatric Use

Of the 1169 adult cancer patients treated with AKYNZEO capsules in clinical studies, 18% were aged 65 and over, while 2% were aged 75 years and over. The nature and frequency of adverse reactions were similar in elderly and younger patients. Exploratory analyses of the impact of age on efficacy were performed in the two trials that compared AKYNZEO to palonosetron [see Clinical Studies (14)]. In Study 1 in patients treated with cisplatin chemotherapy, among the patients less than age 65 years, 115 were treated with AKYNZEO and 116 were treated with palonosetron alone. Among the patients 65 years or older, 20 were treated with AKYNZEO and 20 were treated with palonosetron alone. The difference in Complete Response (CR) rates between AKYNZEO and palonosetron alone was similar between the two age groups in both the acute and delayed phases. In Study 2 in patients treated with anthracyclines plus cyclophosphamide chemotherapy, among the patients less than age 65 years, 608 were treated with AKYNZEO and 602 were treated with palonosetron alone. Among the patients 65 years or older, 116 were treated with AKYNZEO and 123 were treated with palonosetron alone. The difference in CR rates between AKYNZEO and palonosetron alone (4% in <65 years and 2% in >65 years) was similar between the two age groups in the acute phase. In the delayed phase, the difference in CR rates between AKYNZEO and palonosetron alone (9% in <65 years and 1% in ≥ 65 years) was numerically higher in patients <65 years. This difference between age groups in the delayed phase of Study 2 may be explained, in part, by higher CR in the delayed phase associated with palonosetron alone in the older age group (81%) relative to the younger patients treated with palonosetron alone (67%).

Of the 239 adult cancer patients treated with AKYNZEO for injection in clinical studies, 36% were aged 65 and over, while 4% were aged 75 years and over. The nature and frequency of adverse reactions were similar in elderly and younger patients.

In general, use caution when dosing elderly patients as they have a greater frequency of decreased hepatic, renal or cardiac function and concomitant disease or other drug therapy.

8.6 Hepatic Impairment

No dosage adjustment for AKYNZEO is necessary for patients with mild to moderate hepatic impairment (Child-Pugh score 5 to 8). Limited data are available with AKYNZEO in patients with severe hepatic impairment (Child-Pugh score greater than 9). Avoid use of AKYNZEO in patients with severe hepatic impairment [see Overdosage (10), Clinical Pharmacology (12.3)].

8.7 Renal Impairment

No dosage adjustment for AKYNZEO is necessary in patients with mild to moderate renal impairment (creatinine clearance of 30 to 60 mL/min). The pharmacokinetics and safety of netupitant have not been studied in patients with severe renal impairment. Severe renal impairment (creatinine clearance < 30 mL/min) did not substantially affect pharmacokinetics of palonosetron. The pharmacokinetics for netupitant and palonosetron were not studied in patients with end-stage renal disease requiring hemodialysis. Avoid use of AKYNZEO in patients with severe renal impairment or end-stage renal disease [see Clinical Pharmacology (12.3)].

10 OVERDOSAGE

In the event of overdose, AKYNZEO should be discontinued and general supportive treatment and monitoring should be provided. Because of the antiemetic activity of AKYNZEO, drug- induced emesis may not be effective. Dialysis studies have not been performed; due to the large volume of distribution, dialysis is unlikely to be an effective treatment for AKYNZEO overdose.

A total of 33 adult cancer patients were administered oral palonosetron at a dose of 90 mcg/kg (approximately 12 times the recommended dose in AKYNZEO capsules), as part of a dose ranging study and had a similar incidence of adverse reactions compared to lower doses. A single dose of 600 mg (2 times the recommended dose in AKYNZEO capsules) of oral netupitant was administered to 49 healthy subjects and a similar incidence of adverse reactions was observed when compared to lower doses of netupitant in cancer patients and healthy subjects.

11 DESCRIPTION

AKYNZEO (300 mg netupitant/0.5 mg palonosetron) capsules are an oral combination product of netupitant, a substance P/neurokinin 1 (NK-1) receptor antagonist, and palonosetron hydrochloride, a serotonin-3 (5-HT3) receptor antagonist. Both netupitant and palonosetron hydrochloride are anti-nausea and anti-emetic agents.

Netupitant is chemically described: 2-[3,5-bis(trifluoromethyl)phenyl]-N, 2 dimethyl-N-[4-(2-methylphenyl)-6-(4-methylpiperazin-1-yl)pyridin-3-yl] propanamide. The empirical formula is C30H32F6N4O, with a molecular weight of 578.61. Netupitant exists as a single isomer and has the following structural formula:

Palonosetron hydrochloride is chemically described: (3aS)-2-[(S)-1-Azabicyclo [2.2.2]oct-3-yl]-2,3,3a,4,5,6-hexahydro-1-oxo-1H-benz[de]isoquinoline hydrochloride. The empirical formula is C19H24N2O.HCl, with a molecular weight of 332.87. Palonosetron hydrochloride exists as a single isomer and has the following structural formula:

Netupitant is white to off-white crystalline powder. It is freely soluble in toluene and acetone, soluble in isopropanol and ethanol, and very slightly soluble in water.

Palonosetron hydrochloride is a white to off-white crystalline powder. It is freely soluble in water, soluble in propylene glycol, and slightly soluble in ethanol and 2-propanol.

Each AKYNZEO capsule is composed of one white-caramel hard gelatin capsule which contains three tablets each containing 100 mg netupitant and one gelatin capsule containing 0.5 mg palonosetron (equivalent to 0.56 mg palonosetron hydrochloride). The inactive ingredients are butylated hydroxyanisole (BHA), croscarmellose sodium, gelatin, glycerin, magnesium stearate, microcrystalline cellulose, mono- and di-glycerides of capryl/capric acid, polyglyceryl dioleate, povidone K-30, purified water, red iron oxide, silicon dioxide, sodium stearyl fumarate, sorbitol, sucrose fatty acid esters, titanium dioxide and yellow iron oxide. It may contain traces of medium-chain triglycerides, lecithin, and denatured ethanol.

AKYNZEO (235 mg fosnetupitant/0.25 mg palonosetron) for injection is a combination product of fosnetupitant, a prodrug of netupitant, which is a substance P/neurokinin 1 (NK-1) receptor antagonist, and palonosetron hydrochloride, a serotonin-3 (5-HT3) receptor antagonist.

Fosnetupitant chloride hydrochloride is chemically described as 2-(3,5-bis-trifluoromethylphenyl)-N-methyl-N-[6-(4-methyl-4-O-methylene-phosphatepiperazinium-1-yl)-4-o-tolyl-pyridin-3-yl]-isobutyramide chloride hydrochloride. The empirical formula is C31H36F6N4O5P•Cl•HCl, with a molecular weight of 761.53. Fosnetupitant chloride hydrochloride exists as a single isomer and has the following structural formula:

Fosnetupitant chloride hydrochloride is white to off-white to yellowish solid or powder. Its solubility is pH dependent: at acidic pH (pH 2), its solubility is 1.4 mg/mL; at basic pH (pH 10), its solubility is 11.5 mg/mL.

Palonosetron hydrochloride is described above in this section.

AKYNZEO for injection is available for intravenous infusion supplied as a sterile lyophilized powder. Each vial of AKYNZEO for injection contains 235 mg of fosnetupitant (equivalent to 260 mg fosnetupitant chloride hydrochloride) and 0.25 mg of palonosetron (equivalent to 0.28 mg of palonosetron hydrochloride). The inactive ingredients are edetate disodium (6.4 mg), mannitol (760 mg), sodium hydroxide and/or hydrochloric acid (for pH adjustment).

AKYNZEO injection is available for intravenous infusion supplied as a sterile solution in a single-dose vial. Each vial of AKYNZEO injection contains 235 mg of fosnetupitant (equivalent to 260 mg fosnetupitant chloride hydrochloride) and 0.25 mg of palonosetron (equivalent to 0.28 mg of palonosetron hydrochloride). The inactive ingredients are edetate disodium (3.2 mg), mannitol (760 mg), water for injection, sodium hydroxide and/or hydrochloric acid (for pH adjustment).

12 CLINICAL PHARMACOLOGY

12.1 Mechanism of Action

Netupitant is a selective antagonist of human substance P/neurokinin 1 (NK-1) receptors.

Palonosetron is a 5-HT3 receptor antagonist with a strong binding affinity for this receptor and little or no affinity for other receptors. Cancer chemotherapy may be associated with a high incidence of nausea and vomiting, particularly when certain agents, such as cisplatin, are used. 5-HT3 receptors are located on the nerve terminals of the vagus in the periphery and centrally in the chemoreceptor trigger zone of the area postrema. Chemotherapeutic agents produce nausea and vomiting by stimulating the release of serotonin from the enterochromaffin cells of the small intestine. Serotonin then activates 5-HT3 receptors located on vagal afferents to initiate the vomiting reflex. The development of acute emesis is known to depend on serotonin and its 5-HT3 receptors have been demonstrated to selectively stimulate the emetic response.

Delayed emesis has been largely associated with the activation of tachykinin family neurokinin 1 (NK-1) receptors (broadly distributed in the central and peripheral nervous systems) by substance P. As shown in in vitro and in vivo studies, netupitant inhibits substance P mediated responses.

12.2 Pharmacodynamics

NK-1 Receptor Occupancy

The receptor occupancy of netupitant was measured in a human Positron Emission Tomography (PET) study. Netupitant was shown to cross the blood brain barrier with a NK-1 receptor occupancy of 92.5%, 86.5%, 85.0%, 78.0%, and 76.0% in striatum at 6, 24, 48, 72, and 96 hours, respectively, after oral administration of 300 mg netupitant.

Cardiac Electrophysiology

An AKYNZEO oral dose of 600 mg netupitant (2 times the recommended dose) and 1.5 mg palonosetron (3 times the recommended dose) did not prolong the QT interval to any clinically relevant extent.

The recommended dose of AKYNZEO for injection (235 mg fosnetupitant and 0.25 mg palonosetron) did not prolong the QT interval to any clinically relevant extent.

12.3 Pharmacokinetics

Netupitant and Palonosetron

Absorption

Upon single oral administration of AKYNZEO capsules to healthy subjects and patients, netupitant and palonosetron were measurable within 1 hour after administration and reached the maximum concentration (Cmax) in approximately 4 to 5 hours (Table 8).

Table 8: Systemic Exposure (AUCinf and Cmax) of Netupitant and Palonosetron After a Single Oral Dose of AKYNZEO in Healthy Subjects and Cancer Patients
Parameter | Population | Mean (CV%^2 [^1 median (min-max); ^2CV: coefficient of variation; AUCinf: area under the plasma concentration-time curve from time 0 to infinity; tmax: time to maximum concentration.])
Parameter | Population | Netupitant | Palonosetron
AUCinf (ng×h/mL) | Healthy Subjects | 14,402 (51) | 56.7 (33)
AUCinf (ng×h/mL) | Patients | 17,365 (39) | 58.3 (50)
Cmax (ng/mL) | Healthy Subjects | 434 (56) | 1.53 (25)
Cmax (ng/mL) | Patients | 496 (49) | 0.95 (35)
tmax (h) | Healthy Subjects | 5 (2 to 12) | 5 (1 to 12)
tmax (h) | Patients | 4 (2 to 8) | 5 (1 to 12)

Following oral administration, the absolute bioavailability of palonosetron was approximately 97%.

When AKYNZEO capsules were administered under fed conditions, the systemic exposure to netupitant and palonosetron was similar to the exposure under fasting conditions.

In cancer patients who received a single dose of AKYNZEO capsules 1 hour prior to chemotherapy (docetaxel, etoposide, or cyclophosphamide), the Cmax and the area under the concentration-time curve from time zero to infinity (AUCinf) of netupitant and its metabolites were similar to those in healthy subjects. The mean Cmax and AUCinf of palonosetron in cancer patients were similar to those in healthy subjects.

No changes in pharmacokinetics of netupitant and palonosetron were observed when 450 mg oral netupitant and 0.75 mg oral palonosetron were given alone or co-administered (1.5 times the recommended dose of AKYNZEO capsules).

Dose Proportionality

Netupitant

There was a greater than dose-proportional increase in the systemic exposure (108-fold AUCinf increase for a 30-fold dose increase) when the oral netupitant dose was increased from 10 mg (approximately 3% the recommended dose in AKYNZEO capsules) to 300 mg of netupitant and a dose-proportional increase in the systemic exposure when the netupitant dose was increased from 300 mg to 450 mg of netupitant (1.5 times the recommended dose in AKYNZEO capsules).

Palonosetron

After single oral doses of palonosetron ranging from 0.25 to 6.8 mg (0.5 to 13.6 times the recommended dose in AKYNZEO capsules) using a buffered solution, the mean Cmax and AUCinf were dose proportional in healthy subjects.

Following single intravenous doses of AKYNZEO for injection in patients or fosnetupitant in healthy subjects, Cmax of netupitant and palonosetron were achieved at the end of the 30-minute infusion (Table 9).

Table 9: Systemic Exposure (AUC0-120 and Cmax) of Netupitant and Palonosetron After a Single Intravenous Dose of AKYNZEO for Injection in Cancer Patients or a Single Intravenous Dose of Fosnetupitant in Healthy Subjects
Parameter | Population | Mean (CV%^2 [^1 median (min-max); ^2CV: coefficient of variation; AUCinf: area under the plasma concentration-time curve from time 0 to infinity; tmax: time to maximum concentration.])
Parameter | Population | Netupitant | Palonosetron
AUC0-120 (ng×h/mL) | Healthy Subjects | 12,012 (19) | --
AUC0-120 (ng×h/mL) | Patients | 8,922 (22) | 28 (28)
Cmax (ng/mL) | Healthy Subjects | 841 (21) | --
Cmax (ng/mL) | Patients | 590 (28) | 0.8 (35)
tmax (h) | Healthy Subjects | 0.5 (0.5 to 0.4) | --
tmax (h) | Patients | 0.6 (0.5 to 4) | 0.6 (0.5 to 6)

Distribution

After single oral administration of AKYNZEO capsules, netupitant and palonosetron were widely distributed throughout the body (Table 10).

Table 10: Volume of Distribution (Vz/F) in Healthy Subjects and Cancer Patients After a Single Oral Dose of AKYNZEO and In Vitro Protein Binding
Parameter | Population | Mean (CV%c [a Concentration range: 10 to 1300 ng/mL; b Concentration range: 100 to 200 ng/mL; c CV: coefficient of variation])
Parameter | Population | Netupitant | Palonosetron
Vz/F (L) | Healthy Subjects | 3314 (53) | 586 (33)
Vz/F (L) | Patients | 1982 (46) | 663 (24)
Plasma Protein Binding | In vitro studies | Netupitant: > 99.5% Major Metabolites: > 97% | 62%

After administration of single dose of AKYNZEO for injection in patients, the mean ± SD of volume of distribution (Vz) of netupitant and palonosetron were 2627 ± 990 L and 594 ± 239 L, respectively, consistent with previous estimates after single oral administration of AKYNZEO capsules in healthy subjects and cancer patients (Table 10).

Elimination – Netupitant

After a single dose of AKYNZEO capsules, netupitant is eliminated from the body in a multi-exponential fashion and the mean ± SD of apparent elimination half-life was of 96 ± 59 hours in healthy subjects and 80 ± 29 hours in cancer patients. The mean ± SD of estimated systemic clearance (CL/F) was 26.3 ± 12.5 L/h in healthy subjects and 20.3 ± 9.2 L/h in patients.

In patients, following intravenous infusion of AKYNZEO for injection, the mean ± SD total body clearance (CL) and terminal half-life (t1/2) of netupitant were 14.1 ± 5.3 L/h and 144 ± 73 hours, respectively.

Metabolism

Once absorbed, netupitant is extensively metabolized to form three major metabolites: desmethyl derivative, M1; N-oxide derivative, M2; and OH-methyl derivative, M3. Metabolism is mediated primarily by CYP3A4 and to a lesser extent by CYP2C9 and CYP2D6. Metabolites M1, M2 and M3 were shown to bind to the substance P/neurokinin 1 (NK-1) receptor.

The mean AUCinf for metabolites M1, M2 and M3 was 29%, 14% and 33% of netupitant, respectively. The median tmax for metabolite M2 was 5 hours and was about 17 to 32 hours for metabolites M1 and M3, respectively.

Excretion

After a single oral administration of [^14C]netupitant, approximately half the administered radioactivity was recovered from urine and feces within 120 hours of dosing. The total of 3.95% and 70.7% of the radioactive dose was recovered in the urine and feces collected over 336 hours, respectively, and the mean fraction of an oral dose of netupitant excreted unchanged in urine is less than 1% suggesting renal clearance is not a significant elimination route for the netupitant-related entities. About 86.5% and 4.7% of administered radioactivity was estimated to be excreted via the feces and urine within 30 days post-dose.

Elimination - Palonosetron

Following oral administration of AKYNZEO capsules in healthy subjects and cancer patients, the mean (± SD) of half-life of palonosetron was 44 ± 15 hours and 50 ± 16 hours, respectively, whereas the mean ± SD of total body clearance (CL/F) was 9.6 ± 2.7 L/h and 10.0 ± 3.4 L/h, respectively.

After a single intravenous palonosetron dose of 10 mcg/kg (approximately 3 times the recommended dose in AKYNZEO for injection), the mean ± SD of total body clearance (CL) of palonosetron in healthy subjects was 12.1 ± 3.7 L/h, and renal clearance (CLR) was 5.1 ± 2.1 L/h.

In patients, following intravenous infusion of AKYNZEO for injection, the mean ± SD total body clearance (CL) and terminal half-life (t1/2) of palonosetron were 7.6 ± 2.6 L/h and 58 ± 27 h, respectively.

Metabolism

Palonosetron is eliminated by multiple routes with approximately 50% metabolized to form two primary metabolites: N-oxide-palonosetron and 6-Shydroxy-palonosetron. These metabolites each have less than 1% of the 5-HT3 receptor antagonist activity of palonosetron. In vitro metabolism studies have suggested that CYP2D6 and to a lesser extent CYP3A4 and CYP1A2 are involved in the metabolism of palonosetron. However, clinical pharmacokinetic parameters such as Cmax, AUCinf, CL, CLR, Vz and t1/2 are not significantly different between poor and extensive metabolizers of CYP2D6 substrates.

Excretion

Following administration of a single oral 0.75 mg dose of [^14C]palonosetron (1.5 times the recommended dose in AZKYNZEO capsules) to six healthy subjects, 85% to 93% of the total radioactivity was excreted in urine, and 5% to 8% was eliminated in feces. The amount of unchanged palonosetron excreted in the urine represented approximately 40% of the administered dose.

Fosnetupitant

Absorption

Following single intravenous doses of AKYNZEO for injection in patients (235 mg fosnetupitant and 0.25 mg palonosetron infused in 30 minutes) or fosnetupitant in healthy subjects (235 mg fosnetupitant infused in 30 minutes), maximum concentrations of fosnetupitant were achieved at the end of the 30-minute infusion (Table 11).

Table 11: Systemic Exposure of Fosnetupitant After a Single Intravenous Dose of Fosnetupitant in Healthy Subjects or AKYNZEO for Injection in Cancer Patients
Parameter | Population | Mean (CV%^2 [^1 median (min-max); ^2CV: coefficient of variation; AUCinf: AUC from time 0 to infinity])
Cmax (ng/mL) | Healthy Subjects | 6431 (14)
Cmax (ng/mL) | Patients | 3478 (45)
tmax (h) | Healthy Subjects | 0.5 (0.25 to 0.5)
tmax (h) | Patients | 0.5 (0.5 to 0.6)
AUCinf (ng×h/mL) | Healthy Subjects | 2938 (12)
AUCinf (ng×h/mL) | Patients | 1401 (46)

In cross-study comparisons, the mean Cmax and AUCinf of fosnetupitant were lower in patients than in healthy subjects. Similarly, AUC0-120 and Cmax of netupitant in patients were 26% and 30% lower than in healthy subjects, respectively (Table 9). The differences in systemic exposures to netupitant are clinically insignificant.

In healthy subjects, there was a dose-proportional increase in the systemic exposure when the dose of fosnetupitant was increased from 17.6 mg (7.5% of recommended dose in AKYNZEO for injection) to 353 mg (150% of recommended dose in AKYNZEO for injection).

Distribution

The mean ± SD volume of distribution (Vz) of fosnetupitant in healthy subjects and in patients was 124 ± 76 L and 296 ±535 L, respectively. The human plasma protein binding of fosnetupitant was 92% at 1 micromolar and 95% at 10 micromolar.

Elimination

After intravenous administration of AKYNZEO for injection, fosnetupitant plasma concentrations declined in a biexponential manner. Thirty minutes after the end of the infusion, the mean plasma concentration of fosnetupitant was less than 1% of Cmax.

The mean ± SD of terminal elimination half-life and systemic plasma clearance (CL) of fosnetupitant were respectively 0.75 ± 0.40 hours and 249 ± 270 L/h in cancer patients after a single IV dose of AKYNZEO. They were 0.96 ± 0.55 hours (mean ± SD) and 90 ± 13 L/h in healthy subjects after a single intravenous dose of fosnetupitant.

Metabolism

Fosnetupitant is converted in vivo to netupitant by metabolic hydrolysis. In patients receiving AKYNZEO intravenously, netupitant exposure was 17-fold fosnetupitant exposure, as determined by their AUCinf ratio. Netupitant metabolites M1, M2 and M3 were generated from the released netupitant. In patients, metabolite M1, M2 and M3 exposures were 32%, 21% and 28% of netupitant exposure. The median tmax for M1, M2, and M3 were 12, 2 and 12 hours, respectively.

Specific Populations

Geriatric Patients

In cancer patients receiving AKYNZEO capsules, population pharmacokinetic analysis indicated that age (within the range of 29 to 75 years) did not influence the pharmacokinetics of netupitant or palonosetron. In healthy elderly subjects (greater than 65 years of age) the mean AUCinf and Cmax was 25% and 36% higher, respectively, for netupitant, and 37% and 10% higher, respectively, for palonosetron compared to those in healthy younger adults (22 to 45 years of age). The increase in the systemic exposure to netupitant in the elderly subjects is not considered to be clinically significant.

Male and Female Patients

In a pooled analysis of data following AKYNZEO capsules, the Cmax for netupitant was 35% higher in females than in males while the AUCinf was similar between males and females. In female subjects, the mean AUCinf for palonosetron was 35% higher and the mean Cmax was 26% higher than in male subjects. Sex did not affect the pharmacokinetics of fosnetupitant, netupitant, netupitant metabolites and palonosetron after a single intravenous dose of AKYNZEO in patients. In healthy subjects, no effect of sex was observed on the pharmacokinetics of fosnetupitant, netupitant and its metabolites after a single intravenous dose of fosnetupitant alone. The mean ± SD of netupitant AUCinf and Cmax in patients were 15672 ± 5496 ng×h/mL and 567 ± 174 ng/mL, respectively in males and 15518 ± 4814 ng×h/mL and 609 ± 161 ng/mL, respectively in females.

Patients with Renal Impairment

Population pharmacokinetic analysis showed that mild and moderate renal impairment (creatinine clearance 30 to 60 mL/min) did not significantly affect the pharmacokinetics of netupitant in cancer patients. Netupitant has not been studied in patients with severe renal impairment (creatinine clearance less than 30 mL/min).

Mild to moderate renal impairment does not significantly affect palonosetron pharmacokinetic parameters. In a study with intravenous palonosetron, total systemic exposure to palonosetron increased by approximately 28% in patients with severe renal impairment relative to healthy subjects.

The pharmacokinetics of palonosetron and netupitant have not been studied in subjects with end-stage renal disease (creatinine clearance < 15 mL/min not on dialysis) [see Use in Specific Populations (8.7)].

Patients with Hepatic Impairment

The effects of hepatic impairment on the pharmacokinetics of netupitant and palonosetron were studied following administration of a single oral dose of AKYNZEO to patients with mild (Child-Pugh score 5 to 6), moderate (Child-Pugh score 7 to 9), or severe (Child-Pugh score >9) hepatic impairment.

In patients with mild or moderate hepatic impairment, the mean AUCinf of netupitant was 67% and 86% higher, respectively, than in healthy subjects and the mean Cmax for netupitant was about 40% and 41% higher, respectively, than in healthy subjects.

In patients with mild or moderate hepatic impairment, the mean AUCinf of palonosetron was 33% and 62% higher, respectively, than in healthy subjects and the mean Cmax for palonosetron was about 14% higher and unchanged, respectively, than in healthy subjects.

The pharmacokinetics of netupitant and palonosetron were available from only two patients with severe hepatic impairment. As such the data are too limited to draw a conclusion [see Use in Specific Populations (8.6)].

Drug Interaction Studies

Effect of Netupitant/Fosnetupitant and/or Palonosetron on Other Drugs

CYP3A4

In vitro studies have shown that netupitant and its metabolite M1 are inhibitors of CYP3A4. An in vivo study has confirmed that netupitant is a moderate inhibitor of CYP3A4.

Dexamethasone

In healthy subjects, the oral administration of a single AKYNZEO capsule with the CYP3A4 substrate dexamethasone (12 mg on day 1 followed by once-a-day administrations of 8 mg on days 2, 3, 4, 6, 8 and 10), increased the plasma concentrations of dexamethasone for 6 days (Table 12).

Table 12: Effect of a Single Dose of Oral AKYNZEO (Day 1) on the Systemic Exposure of a Co-administered CYP3A4 Substrate (Dexamethasone) in Healthy Subjects
% Change for Dexamethasone
Day 1 |  | Day 4 |  | Day 6 |  | Day 8
Cmax | AUC0-t | Cmax | AUC0-t | Cmax | AUC0-t | Cmax | AUC0-t
2%↓ | 58%↑ | 54%↑ | 139%↑ | 29%↑ | 49%↑ | 7%↑ | 20%↑
*the interacting drug (dexamethasone 12 mg) was administered on day 1 with AKYNZEO and alone (8 mg) on days 2, 3, 4, 6, 8 and 10; AUC0-t: AUC from time zero to time t of last measurable concentration after dexamethasone administration on Days 1, 4, 6 and 8
↑ = Increased; ↓ = Decreased

In healthy subjects, co-administration of a single intravenous fosnetupitant dose (235 mg) with a 20 mg oral dexamethasone on day 1 followed by twice-a-day administrations of 8 mg dexamethasone on days 2, 3, and 4, increased dexamethasone exposure 2.4-fold on day 4 (Table 13).

Table 13: Effect of a Single 235 mg Dose of Intravenous Fosnetupitant (Day 1) on the Systemic Exposure of a Co-administered CYP3A4 Substrate (Dexamethasone) in Healthy Subjects
% Change for Dexamethasone
Day 1 |  | Day 4
Cmax | AUC0-24 | Cmax | AUC84-108
3%↓ | 50%↑ | 70%↑ | 142%↑
*the interacting drug (dexamethasone 20 mg) was administered on day 1 with AKYNZEO and alone (8 mg bid) on Days 2, 3, 4; AUC0-24: AUC from time 0 to 24h after dexamethasone administration on Day 1; AUC84-108: AUC from time 84h to 108h after dexamethasone administration on Day 4
↑ = Increased; ↓ = Decreased

Considering the limited fosnetupitant exposure in human plasma and its conversion to netupitant within 30 minutes after completion of infusion, the effects are ascribed to netupitant [see Drug Interactions (7.1)].

Midazolam

When co-administered with netupitant 300 mg the mean Cmax and AUCinf of midazolam after single dose oral administration of 7.5 mg midazolam was 36% and 126% higher, respectively [see Drug Interactions (7.1)].

Chemotherapeutic Agents (docetaxel, etoposide, cyclophosphamide)

Systemic exposure to intravenously administered chemotherapeutic agents that are metabolized by CYP3A4 was higher when AKYNZEO capsules was co-administered in cancer patients than when palonosetron alone was co-administered (see Table 14).

Table 14: Effect of a Single Dose of Oral AKYNZEO on the Systemic Exposure of Co-administered Chemotherapy Agents Metabolized by CYP3A4 in Patients with Cancer
Co-administered Chemotherapeutic Agenta [a Following a single oral dose of AKYNZEO compared to co-administered with palonosetron alone bAUC0-t: AUC from time zero to time t of last measurable concentration ↑ = Increased; ↓ = Decreased] | Change in Systemic Exposures of Chemotherapeutic Agents when Co-administered with AKYNZEO Capsules Compared to Co-administration with Palonosetron
Co-administered Chemotherapeutic Agenta [a Following a single oral dose of AKYNZEO compared to co-administered with palonosetron alone bAUC0-t: AUC from time zero to time t of last measurable concentration ↑ = Increased; ↓ = Decreased] | AUC0-tb | Cmax
Docetaxel 75 to 100 mg/m^2 | 35%↑ | 49%↑
Etoposide 35 to 100 mg/m^2 | 28%↑ | 10%↑
Cyclophosphamide 500 to 1000 mg/m^2 | 20%↑ | 27%↑

The mean AUCinf of palonosetron was about 65% higher when AKYNZEO capsules was co-administered with docetaxel than with etoposide or cyclophosphamide, while the mean AUCinf of netupitant was similar among groups that received docetaxel, etoposide, or cyclophosphamide [see Drug Interactions (7.1)].

Erythromycin

When 500 mg erythromycin was co-administered with netupitant 300 mg, the systemic exposure of erythromycin was highly variable and the mean Cmax and AUCinf of erythromycin were increased by 92% and 56%, respectively. The change in exposure is not clinically significant.

Oral Contraceptives

A single dose of AKYNZEO capsules, when given with a single oral dose of 60 mcg ethinyl estradiol and 300 mcg levonorgestrel, showed no effect on Cmax and increased the AUC0-t of levonorgestrel by 46%. The Cmax and AUC0-t of ethinyl estradiol increased by 5% and 16% respectively. The change in exposure is not clinically significant [see Drug Interactions (7.1)].

Other CYP P450 enzymes

Based on the in vitro studies, netupitant, and its metabolites are unlikely to have in vivo drug-drug interaction via inhibition of CYP1A2, CYP2B6, CYP2C8, CYP2C9, CYP2C19, and CYP2D6 at the clinical dose of oral AKYNZEO.

Netupitant and its metabolites, M1, M2 and M3, are not inducers of CYP1A2, CYP2B6, CYP2C9, CYP2C19 and CYP3A4.

In in vitro studies, palonosetron did not inhibit CYP1A2, CYP2A6, CYP2B6, CYP2C9, CYP2D6, CYP2E1 and CYP3A4/5 or induce CYP1A2, CYP2D6 or CYP3A4/5. CYP2C19 was not investigated.

Transporters P-gp and BCRP

Based on in vitro studies, netupitant is an inhibitor of P-glycoprotein (P-gp) and breast cancer resistant protein (BCRP) transporters. In vitro studies indicated that fosnetupitant is an inhibitor of P-gp. However, an in vivo interaction between AKYNZEO for injection and P-gp substrates is considered unlikely.

In vitro, palonosetron was an inhibitor of MATE1, MATE2-K, OCT1, OCT2 and OAT3 transporters. An in vivo interaction between AKYNZEO capsules or injection and transporter substrates is considered unlikely.

Digoxin P-gp Substrate

Co-administration of oral netupitant 450 mg (1.5 times the recommended dose in AKYNZEO capsules) did not significantly affect the systemic exposure (4% increase of AUC0-24 at steady state) and urinary excretion (2% increase) of oral digoxin, a substrate of P-gp, at steady-state. Concurrent administration of AKYNZEO capsules or AKYNZEO for injection with digoxin is not expected to affect the systemic exposure to digoxin.

Other Transporters

In vitro studies indicate that netupitant and its three major metabolites are unlikely to have in vivo drug-drug interactions with human efflux transporters BSEP, MRP2, and human uptake transporters OATP1B1, OATP1B3, OAT1, OAT3, OCT1, and OCT2 at the clinical dose of 300 mg.

In vitro studies indicated that fosnetupitant is an inhibitor of OATP1B1 and OATP1B3 transporters. However, an in vivo interaction between AKYNZEO for injection and OATP1B1, OATP1B3, and P-gp substrates is considered unlikely.

In vitro studies indicated that fosnetupitant is not an inhibitor of MATE2-K transporter.

Effects of Other Drugs on Netupitant/Fosnetupitant and/or Palonosetron

Based on in vitro studies, fosnetupitant is not a substrate of BCRP, BSEP, MDR1 and MATE1, MATE2-K, OAT1, OAT3, OATP2B1, OCT1 and OCT2.

Netupitant is not a substrate for P-gp. However, metabolite M2 is a substrate for P-gp.

Netupitant and palonosetron are CYP3A4 substrates. Co-administration of strong CYP3A4 inhibitors, such as ketoconazole, or strong CYP3A4 inducers, such as rifampin, with a single oral administration of AKYNZEO capsules affects with clinical significance the exposure to netupitant but not to palonosetron (Table 15).

Table 15: Change in Systemic Exposure to Netupitant and Palonosetrona When a Single Dose of AKYNZEO is Co‑Administered with Either a CYP3A4 Inhibitor or a CYP3A4 Inducer in Healthy Subjects
Co-administered Drug | Netupitantb [a Following a single oral dose of AKYNZEO; b Geometric Mean AUCinf and Cmax; ↑ = Increased; ↓ = Decreased] |  | Palonosetronb
Co-administered Drug | AUCinf | Cmax | AUCinf | Cmax
Strong CYP3A4 Inhibitor
Ketoconazole 400 mg once daily for 12 days | 140%↑ | 25%↑ | 10%↑ | 15%↑
Strong CYP3A4 Inducer
Rifampin 600 mg once daily for 17 days | 62%↓ | 82%↓ | 19%↓ | 15%↓

13 NONCLINICAL TOXICOLOGY

13.1 Carcinogenesis, Mutagenesis, Impairment of Fertility

Netupitant

Long-term studies in animals to evaluate carcinogenic potential have not been performed with netupitant. Netupitant was not genotoxic in the Ames test, the mouse lymphoma cell mutation test, or the in vivo rat micronucleus test.

Daily oral administration of netupitant in rats at doses up to 30 mg/kg (1.9 times the human AUC in male rats and 3.7 times the human AUC in female rats at the recommended dose) had no effects on fertility or reproductive performance.

Fosnetupitant

Long-term studies in animals to evaluate carcinogenic potential have not been performed with fosnetupitant.

Fosnetupitant was not genotoxic in the Ames test and in vivo rat micronucleus test. In human lymphocytes, fosnetupitant did not induce structural chromosomal aberrations.

Daily intravenous administration of fosnetupitant in rats at doses up to 39 mg/kg (1.3 times the human AUC for fosnetupitant and 4.3 times the human AUC for netupitant at the recommended single dose to be given with each cycle of chemotherapy) had no effects on fertility or reproductive performance.

Palonosetron

In a 104-week carcinogenicity study in CD-1 mice, animals were treated with oral doses of palonosetron at 10, 30, and 60 mg/kg/day. Treatment with palonosetron was not tumorigenic. The highest tested dose produced a systemic exposure to palonosetron (plasma AUC) of about 90 to 173 times the human exposure (AUC=49.7 ng•h/mL) at the recommended oral dose of 0.5 mg. In a 104-week carcinogenicity study in Sprague-Dawley rats, male and female rats were treated with oral doses of 15, 30, and 60 mg/kg/day and 15, 45, and 90 mg/kg/day, respectively. The highest doses produced a systemic exposure to palonosetron (plasma AUC) of 82 and 185 times the human exposure at the recommended dose. Treatment with palonosetron produced increased incidences of adrenal benign pheochromocytoma and combined benign and malignant pheochromocytoma, increased incidences of pancreatic Islet cell adenoma and combined adenoma and carcinoma and pituitary adenoma in male rats. In female rats, it produced hepatocellular adenoma and carcinoma and increased the incidences of thyroid C-cell adenoma and combined adenoma and carcinoma.

Palonosetron was not genotoxic in the Ames test, the Chinese hamster ovarian cell (CHO/HGPRT) forward mutation test, the ex vivo hepatocyte unscheduled DNA synthesis (UDS) test, or the mouse micronucleus test. It was, however, positive for clastogenic effects in the Chinese hamster ovarian (CHO) cell chromosomal aberration test. Palonosetron at oral doses up to 60 mg/kg/day (about 921 times the recommended oral dose based on body surface area) was found to have no effect on fertility and reproductive performance of male and female rats.

14 CLINICAL STUDIES

Study 1

In a multicenter, randomized, parallel, double-blind, controlled clinical trial of 694 patients, the efficacy and safety of a single dose of oral netupitant in combination with oral palonosetron was compared with a single oral dose of palonosetron in cancer patients receiving a chemotherapy regimen that included cisplatin (median dose of 75 mg/m^2). The efficacy of AKYNZEO was assessed in 135 patients who received AKYNZEO capsules (300 mg netupitant and 0.5 mg palonosetron) and 136 patients who received oral palonosetron 0.5 mg.

Treatment regimens for the AKYNZEO and palonosetron arms are summarized in Table 16.

Table 16: Oral Antiemetic Treatment Regimen in Study 1
Treatment Regimen | Day 1 | Days 2 to 4
AKYNZEO | AKYNZEO capsules: 300 mg neupitant/; 0.5 mg palonosetron; Dexamethasone 12 mg | Dexamethasone 8 mg once a day
Palonosetron | Palonosetron 0.5 mg; Dexamethasone 20 mg | Dexamethasone 8 mg twice a day

Of the 135 patients who received AKYNZEO, 43% were women, and all patients were White. The age ranged from 19 to 77 years, with a median age of 53 years.

During the study, 86% of the 135 treated patients in the AKYNZEO arm received a concomitant chemotherapeutic agent in addition to protocol-mandated cisplatin. The most common chemotherapeutic agents and the proportion of patients exposed were cyclophosphamide (34%), fluorouracil (24%), etoposide (21%), and doxorubicin (16%).

The key efficacy endpoints were complete response (CR) (defined as no emetic episode and no use of rescue medication) for the 25 to 120 hour interval (delayed phase), CR for the 0 to 24 hour interval (acute phase), and CR within 120 hours (overall phase) after the start of the chemotherapy administration.

A summary of the key results from this study is shown in Table 17.

Table 17: Proportion of Patients Responding by Treatment Group and Phase in Study 1
 | AKYNZEO Capsules 300 mg netupitant/ 0.5 mg palonosetron (N=135) | Palonosetron 0.5 mg (N=136) | p-value [Adjusted p-values for multiple comparisons using Cochran Mantel Haenszel test, stratified by gender.]
COMPLETE RESPONSE
Delayed Phase [Delayed phase: 25 to 120 hours post-cisplatin treatment.] | 90.4 | 80.1 | 0.032
Acute Phase [Acute phase: 0 to 24 hours post-cisplatin treatment.] | 98.5 | 89.7 | 0.002
Overall Phase [Overall: 0 to 120 hours post-cisplatin treatment.] | 89.6 | 76.5 | 0.003

Study 2 (NCT01339260)

In a multicenter, randomized, parallel, double-blind, active controlled, superiority trial, the efficacy and safety of a single oral dose of AKYNZEO was compared with a single oral dose of palonosetron 0.5 mg in cancer patients scheduled to receive the first cycle of an anthracycline and cyclophosphamide (AC) regimen for the treatment of a solid malignant tumor (Study 2). All patients received a single oral dose of dexamethasone. Treatment regimens for the AKYNZEO and palonosetron arms are summarized in Table 18.

Table 18: Oral Antiemetic Treatment Regimen in Study 2
Treatment Regimen | Day 1 | Days 2 to 3
AKYNZEO | AKYNZEO capsules: 300 mg netupitant/; 0.5 mg palonosetron; Dexamethasone 12 mg | No antiemetic treatment
Palonosetron | Palonosetron 0.5 mg; Dexamethasone 20 mg | No antiemetic treatment

After completion of cycle 1, patients had the option to participate in a multiple-cycle extension, receiving the same treatment as assigned in cycle 1. There was no pre-specified limit of the number of repeat consecutive cycles for any patient.

A total of 1455 patients were randomized to the AKYNZEO arm or palonosetron arm. A total of 1450 patients (AKYNZEO n=725; palonosetron n=725) received study medication: of these, 1438 patients (99%) completed cycle 1 and 1286 patients (88%) continued treatment in the multiple‑cycle extension. A total of 907 patients (62%) completed the multiple‑cycle extension up to a maximum of eight treatment cycles.

Of the 725 patients who received AKYNZEO, 711 (98%) were women; 79% were White, 14% Asian, 6% Hispanic, and <1% were Black or Other. Age ranged from 22 to 79 years, with a median age of 54 years. A total of 724 patients (99.9%) were treated with cyclophosphamide. All patients were additionally treated with either doxorubicin (68%) or epirubicin (32%).

During the first cycle, 32% of the 725 patients treated with AKYNZEO received a concomitant chemotherapeutic agent in addition to protocol-mandated regimens, with the most common chemotherapeutic being fluorouracil (28%) and docetaxel (3%).

The primary efficacy endpoint was the CR rate in the delayed phase, 25 to120 hours after the start of chemotherapy administration.

Major secondary efficacy endpoints included CR for the acute and overall phases. A summary of key results from Study 2 is shown in Table 19.

Table 19: Proportion of Patients Responding by Treatment Group and Phase Cycle 1 in Study 2
 | AKYNZEO Capsules 300 mg netupitant/ 0.5 mg palonosetron N=724 % | Palonosetron 0.5 mg N=725 % | p-value [p-value from Cochran Mantel Haenszel test, stratified by age class and region.]
PRIMARY ENDPOINT
COMPLETE RESPONSE
Delayed Phase [Delayed phase: 25 to 120 hours after anthracycline and cyclophosphamide regimen.] | 76.9 | 69.5 | 0.001
MAJOR SECONDARY ENDPOINTS
COMPLETE RESPONSE
Acute Phase [Acute phase: 0 to 24 hours after anthracycline and cyclophosphamide regimen.] | 88.4 | 85.0 | 0.047
Overall Phase [Overall: 0 to 120 hours after anthracycline and cyclophosphamide regimen.] | 74.3 | 66.6 | 0.001

Multiple Cycles

Patients continued into the Multiple-Cycle extension for up to 7 additional cycles of chemotherapy. The proportion of patients with complete response in the delayed phase by treatment group at each cycle (cycles 2 to 6) is displayed in Figure 1. A limited number of patients received treatment beyond cycle 6. During all cycles the CR rate in the delayed phase was higher for AKYNZEO than for palonosetron. Antiemetic activity of AKYNZEO was maintained throughout repeat cycles for those patients continuing in each of the multiple cycles.

Figure 1: Proportion of Patients with Complete Response in the Delayed Phase by Treatment Group and Cycle in Study 2

Additional clinical trials (Study 3 and Study 4) were conducted to support the efficacy of AKYNZEO.

Study 3 (NCT01376297)

In a separate study, 309 patients undergoing initial and repeat cycles of chemotherapy (including carboplatin, cisplatin, oxaliplatin, and doxorubicin regimens) received AKYNZEO; efficacy was maintained throughout all cycles.

Study 4 (NCT01363479)

In a multicenter, multinational, randomized, active‑controlled, double‑blind, double‑dummy, parallel group, clinical non-inferiority study, the efficacy and safety of a single dose of oral palonosetron 0.5 mg was compared to intravenous palonosetron 0.25 mg in cancer patients scheduled to receive highly emetogenic cisplatin (>70 mg/m^2) based chemotherapy. The purpose of this study was to demonstrate that oral palonosetron 0.5 mg contributes to the efficacy of AKYNZEO during the acute phase (first 24 hours after cancer chemotherapy) in the setting of cisplatin based chemotherapy. A total of 739 patients (oral palonosetron n=370; intravenous palonosetron n=369) received study medication.

The primary efficacy endpoint was complete response (CR) (defined as no emetic episode and no use of rescue medication) within 24 hours (acute phase) after the start of cisplatin-based chemotherapy administration. In the oral palonosetron arm, 89.4% of patients achieved a CR in the acute phase compared to 86.2% of patients in the intravenous palonosetron arm, with a difference of 3.2% (99% CI: ‑2.7% to 9.2%). Non‑inferiority of oral palonosetron versus intravenous palonosetron was demonstrated since the lower limit of the two‑sided 99% CI for the difference in proportions of patients with CR was greater (i.e., closer to zero) than the pre‑defined non‑inferiority margin set at ‑15%.

Study 5 (NCT02557035)

In a multicenter, multinational, randomized, active controlled, double blind, double dummy, parallel group, clinical non-inferiority study, the efficacy and safety of a single dose of intravenous palonosetron 0.25 mg administered over 30 minutes (infusion) was compared to intravenous palonosetron 0.25 mg administered over 30 seconds (bolus) in cancer patients scheduled to receive a HEC chemotherapy regimen that included cisplatin administered as a single IV dose of 70 mg/m^2, cyclophosphamide 1500 mg/m^2, carmustine (BCNU) >250mg/m^2, dacarbazine (DTIC) and mechloretamine (nitrogen mustard). The purpose of this study was to demonstrate that intravenous palonosetron 0.25 mg administered over 30 minutes was non-inferior to administration of intravenous palonosetron 0.25 mg administered over 30 seconds for prevention of nausea and vomiting during the acute phase (first 24 hours after cancer chemotherapy) in the HEC setting. A total of 425 patients (intravenous palonosetron infusion n=214; intravenous palonosetron bolus n=211) received study medication and HEC and completed the 0-24 h study period with no major protocol violations and were included in the Per Protocol Population.

The primary efficacy endpoint was complete response (CR defined as no emetic episode and no use of rescue medication) in the 24 hours (acute phase) after the start of the scheduled chemotherapy. In the intravenous palonosetron infusion group, 82.7% of patients achieved CR in the acute phase compared to 86.3% of patients in the intravenous palonosetron bolus group, with a difference of -3.4% (99% CI: - 12.0% to 5.2%). Non-inferiority of administration of intravenous palonosetron over 30 minutes compared to administration of intravenous palonosetron over 30 seconds was demonstrated since the lower limit of the two-sided 99% CI for the difference in proportions of patients with CR was greater (i.e., closer to zero) than the pre-defined non inferiority margin set at -15%.

16 HOW SUPPLIED/STORAGE AND HANDLING

Capsules

AKYNZEO (300 mg netupitant/0.5 mg palonosetron) capsules: hard gelatin capsules with white body and caramel cap with “HE1” printed on the body. They are supplied as follows:

NDC # 69639-101-01: pack of one capsule in one blister

NDC # 69639-101-04: pack of four capsules (two capsules per blister strip).

Storage

AKYNZEO capsules should be stored at 20 °C to 25 °C (68 °F to 77 °F); excursions permitted from 15 °C to 30 °C (59 °F to 86 °F) [see USP Controlled Room Temperature].

For Injection

AKYNZEO (235 mg fosnetupitant/0.25 mg palonosetron) for injection: sterile, white to off-white lyophilized powder in single-dose vial for reconstitution.

NDC # 69639-102-01: pack of one vial of lyophilized powder

Storage

Store AKYNZEO for injection in carton, protected from light at 2° to 8°C (35.6 F to 46.4°F).

Injection (Ready-to-Use and To-be-Diluted)

AKYNZEO 235 mg fosnetupitant/0.25 mg palonosetron per 20 mL (11.75 mg/0.0125 mg per mL) injection: sterile, clear solution in a single-dose vial.

- NDC # 69639-106-01: pack of one vial of solution with hanger (Ready-to-Use)
- NDC # 69639-105-01: pack of one vial of solution (To-be-Diluted)

Storage

Store AKYNZEO injection in carton, protected from light at 20°C to 25°C (68°F to 77°F).

17 PATIENT COUNSELING INFORMATION

Advise patients to read the FDA-approved patient labeling (Patient Information).

Administration

Advise patients to take AKYNZEO capsules with or without food approximately 1 hour prior to the start of chemotherapy [see Dosage and Administration (2.1)].

Hypersensitivity Reactions

Advise patients that hypersensitivity reactions, including anaphylaxis, may occur in patients receiving AKYNZEO. Advise patients to seek immediate medical attention if any signs or symptoms of a hypersensitivity reaction occur while taking AKYNZEO [See Warnings and Precautions (5.1)].

Serotonin Syndrome

Advise patients of the possibility of serotonin syndrome especially with concomitant use of AKYNZEO and another serotonergic agent such as medications to treat depression and migraines. Advise patients to seek immediate medical attention if the following symptoms occur: changes in mental status, autonomic instability, neuromuscular symptoms, with or without gastrointestinal symptoms [see Warnings and Precautions (5.2)].

Pregnancy

Inform female patients of reproductive potential that AKYNZEO may cause fetal harm and to inform their prescriber of a known or suspected pregnancy [see Use in Specific Populations (8.1)].

Manufactured by Helsinn Birex Pharmaceuticals, Dublin, Ireland for Helsinn Healthcare SA, Switzerland

Distributed by Helsinn Therapeutics (U.S.), Inc., Iselin, NJ 08830, under license of Helsinn Healthcare SA, Switzerland

AKYNZEO is a registered trademark of Helsinn Healthcare SA, Lugano, Switzerland

Patient Information
AKYNZEO® (a kin zee oh)
(netupitant and palonosetron) capsules, for oral use
(fosnetupitant and palonosetron) for injection, for intravenous use

(fosnetupitant and palonosetron) injection, for intravenous use

Read this Patient Information before you start receiving AKYNZEO and each time you are scheduled to receive AKYNZEO. There may be new information. This information does not take the place of talking with your doctor about your medical condition or your treatment.

What is AKYNZEO?

AKYNZEO is a prescription medicine called an antiemetic. AKYNZEO is used in combination with the medicine dexamethasone in people to help prevent the nausea and vomiting that happens right away or later with certain anti-cancer medicines (chemotherapy).

It is not known if AKYNZEO is safe and effective in children under 18 years of age.

Before you take or receive AKYNZEO, tell your doctor about all of your medical conditions, including if you:

- have had an allergic reaction to palonosetron or another medicine for nausea or vomiting.
- have liver problems.
- have kidney problems.
- are pregnant or plan to become pregnant. AKYNZEO may harm your unborn baby.
- are breastfeeding or plan to breastfeed. It is not known if AKYNZEO passes into your breast milk. You and your doctor should decide if you will take AKYNZEO or breastfeed. You should not do both.

Tell your doctor about all of the medicines you take, including prescription and over-the-counter medicines, vitamins, and herbal supplements.

AKYNZEO and certain other medicines can affect each other, causing serious side effects.

How will I take or receive AKYNZEO?

- Take AKYNZEO exactly as your doctor tells you to take it.
- Take 1 AKYNZEO capsule by mouth, about 1 hour before you get your anti-cancer medicine (chemotherapy).
- AKYNZEO for injection will be given to you in your vein by I.V. (intravenous) infusion about 30 minutes before you start your chemotherapy treatment.
- Take AKYNZEO capsule with or without food.
- If you take too much AKYNZEO, call your doctor or go to the nearest hospital emergency room right away.

What are the possible side effects of AKYNZEO?

AKYNZEO may cause serious side effects, including:

- allergic reactions, such as anaphylaxis. Get emergency medical help right away if you get any of the following symptoms of a serious allergic reaction with AKYNZEO: hives, swollen face, trouble breathing, or chest pain.
- serotonin syndrome which can happen with AKYNZEO particularly with certain other medicines such as anti-depressants and anti-migraine medicines and can lead to death.
  - Stop taking AKYNZEO capsules and go to the nearest hospital emergency room right away if you get any of the following symptoms of serotonin syndrome: agitation, hallucinations or other changes in mental status, dizziness, fast heartbeat, sweating, high body temperature, shaking (tremors), unsteady movements, muscle twitching (overactive reflexes), or seizures with or without nausea, vomiting, and diarrhea.

The most common side effects of AKYNZEO capsules and injection include: headache, weakness, fatigue, upset stomach, constipation, and skin redness.

These are not all the possible side effects of AKYNZEO. Call your doctor for medical advice about side effects. You may report side effects to FDA at 1-800-FDA-1088.

How should I store AKYNZEO capsules?

Store AKYNZEO at room temperature between 68°F to 77°F (20°C to 25°C).

General information about the safe and effective use of AKYNZEO

Medicines are sometimes prescribed for purposes other than those listed in a Patient Information leaflet. Do not use AKYNZEO for a condition for which it was not prescribed. Do not give AKYNZEO to other people, even if they have the same symptoms that you have. It may harm them. You can ask your doctor or pharmacist for information about AKYNZEO that is written for health professionals.

What are the ingredients in AKYNZEO capsules?

Active ingredients: netupitant and palonosetron hydrochloride

Inactive ingredients: butylated hydroxyanisole (BHA), croscarmellose sodium, gelatin, glycerin, magnesium stearate, microcrystalline cellulose, mono- and di-glycerides of capryl/capric acid, polyglyceryl dioleate, povidone K-30, purified water, red iron oxide, silicon dioxide, sodium stearyl fumarate, sorbitol, sucrose fatty acid esters, titanium dioxide and yellow iron oxide. It may contain traces of medium-chain triglycerides, lecithin, and denatured ethanol. AKYNZEO may contain small amounts of medium-chain triglycerides, lecithin, and denatured ethanol.

What are the ingredients in AKYNZEO for injection?

Active ingredients: fosnetupitant chloride hydrochoride and palonosetron hydrochloride

Inactive ingredients: mannitol, edetate disodium, sodium hydroxide, and hydrochloric acid may be added for pH adjustment.

What are the ingredients in AKYNZEO injection?

Active ingredients: fosnetupitant chloride hydrochloride and palonosetron hydrochloride
Inactive ingredients: edetate disodium, mannitol and water for injection; sodium hydroxide and hydrochloric acid may be added for pH adjustment.

Manufactured by Helsinn Birex Pharmaceuticals, Dublin, Ireland

for Helsinn Healthcare SA, Switzerland

Distributed by Helsinn Therapeutics (U.S.), Inc. Iselin, NJ 08830 under license of Helsinn Healthcare SA, Switzerland

AKYNZEO is a registered trademark of Helsinn Healthcare SA, Lugano, Switzerland

For more information, go to www.akynzeo.com

This Patient Information has been approved by the U.S. Food and Drug Administration. Approved: May 2022

Instructions for opening the AKYNZEO pack of one capsule in one blister:

1. Press buttons A and B together with one hand.

2. Pull the tab card on the right hand side with other hand.

3. Release buttons A and B while pulling the tab card.

4. Keep pulling the tab card until the pack is fully open.

PACKAGE LABEL

Principal Display Panel
NDC 69639-101-01
Akynzeo
(netupitant and palonosetron)
capsules, 300mg/0.5mg

PACKAGE LABEL

Principal Display Panel
NDC 69639-101-04
Akynzeo
(netupitant and palonosetron)
capsules, 300mg/0.5mg
For Hospital Use Only

PACKAGE LABEL

Principal Display Panel
NDC 69639-102
Akynzeo
(fosnetupitant and palonosetron) for injection
235mg/0.25mg per vial

PACKAGE LABEL

Principal Display Panel
NDC 69639-105
Akynzeo
(fosnetupitant and palonosetron) injection
235mg/0.25mg per vial

Must be diluted. For intravenous infusion only

PACKAGE LABEL

Principal Display Panel
NDC 69639-105
Akynzeo
(fosnetupitant and palonosetron) injection
235mg/0.25mg per vial

Must be diluted. For intravenous infusion only
Must be diluted. For intravenous infusion only

PACKAGE LABEL

Principal Display Panel
Label

NDC 69639-106
Akynzeo
(fosnetupitant and palonosetron) injection
235mg/0.25mg per 20mL

For intravenous infusion only.

Ready-to-Use Formulation and does NOT require further dilution

Principal Display Panel
Carton

NDC 69639-106
Akynzeo
(fosnetupitant and palonosetron) injection
235mg/0.25mg per 20mL

For intravenous infusion only.

Ready-to-Use Formulation and does NOT require further dilution